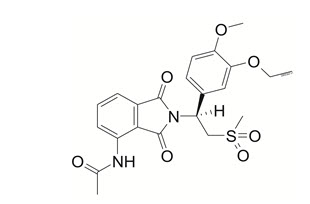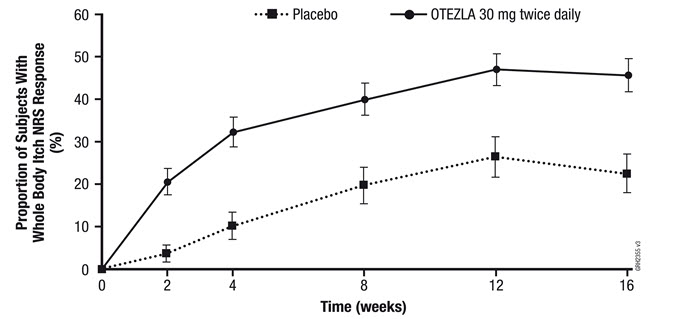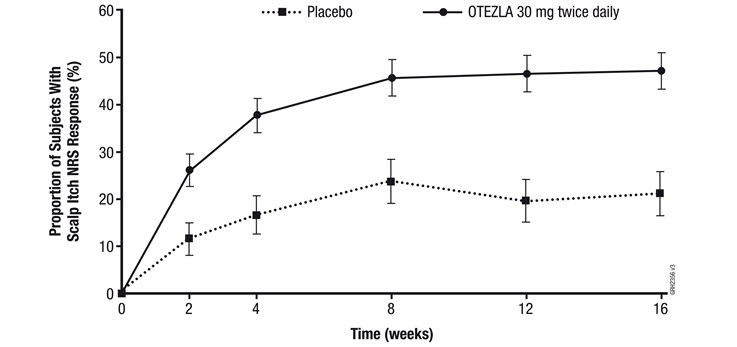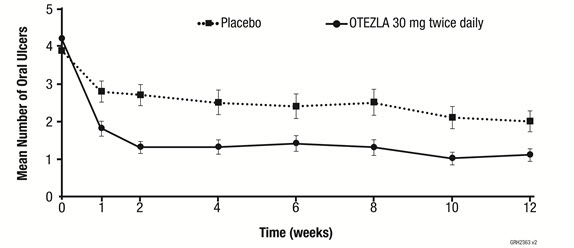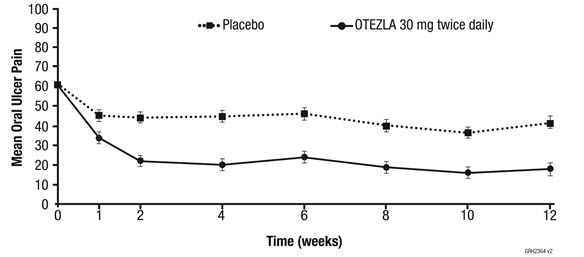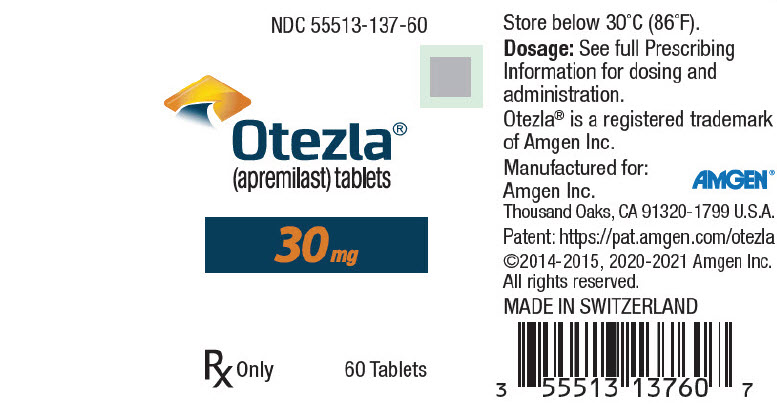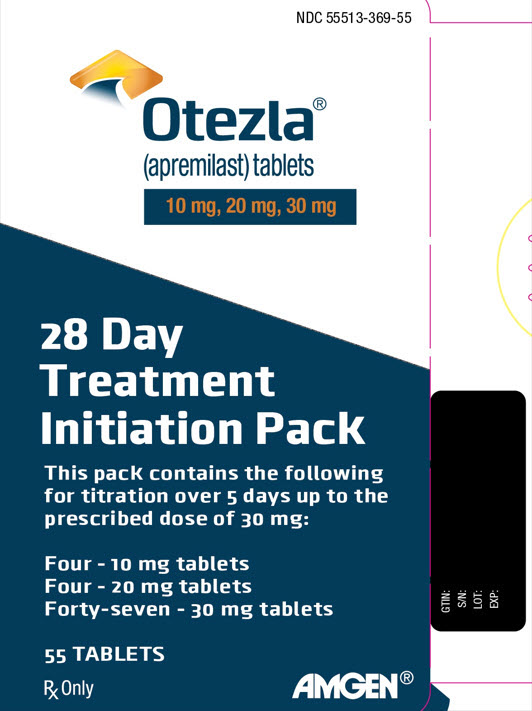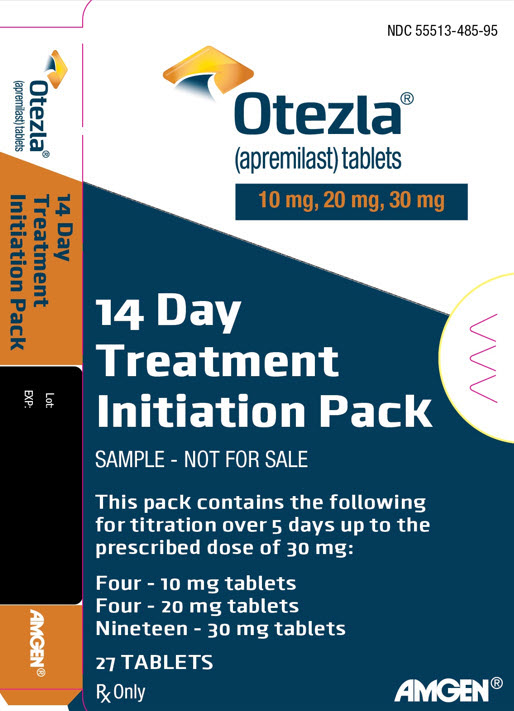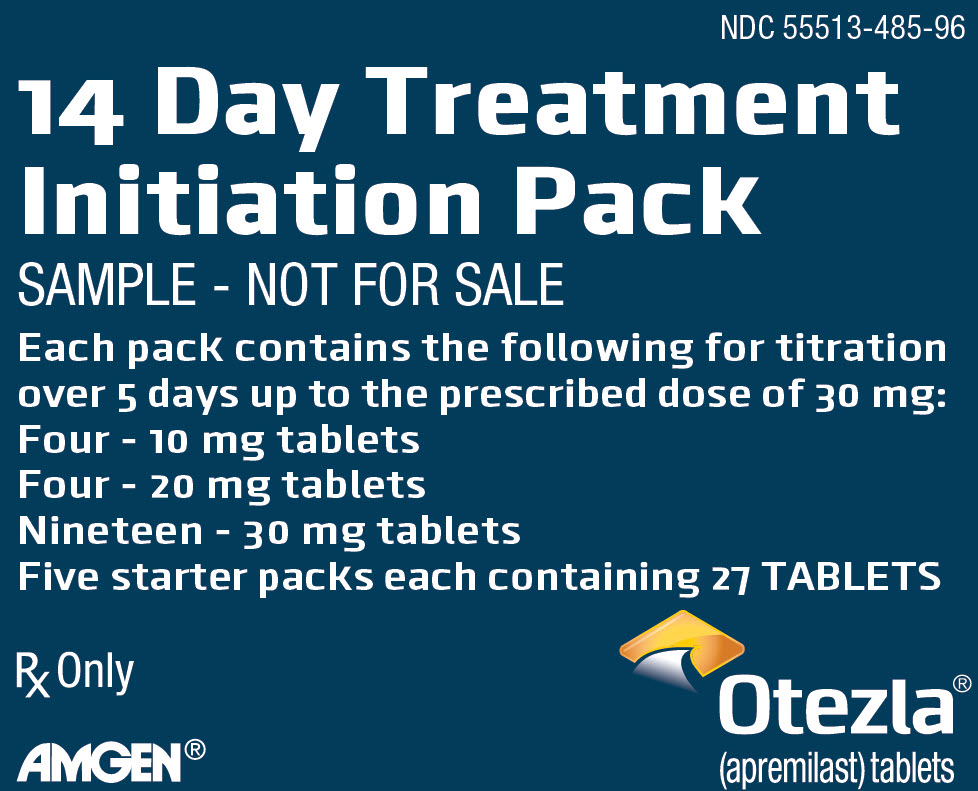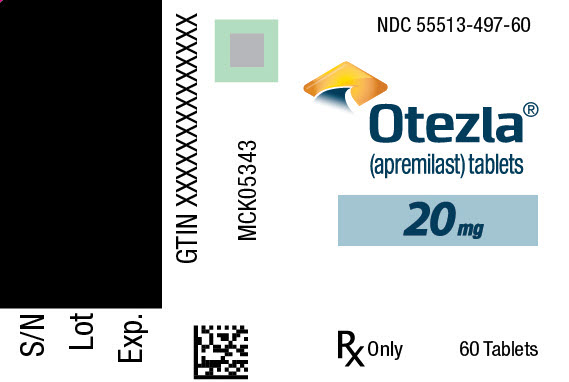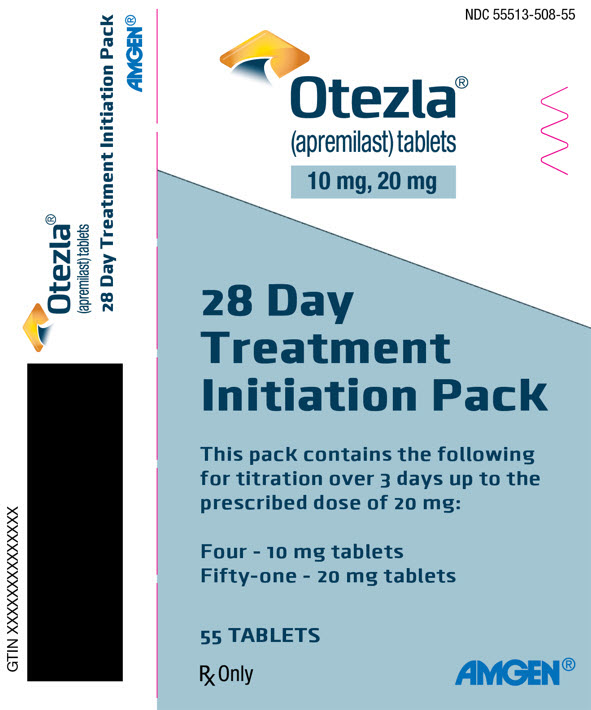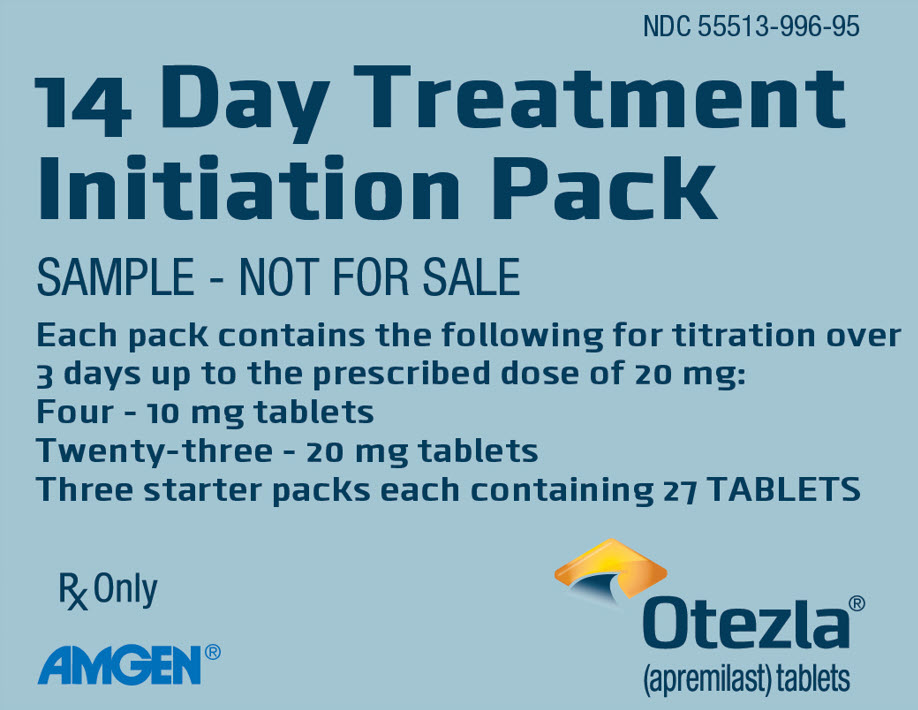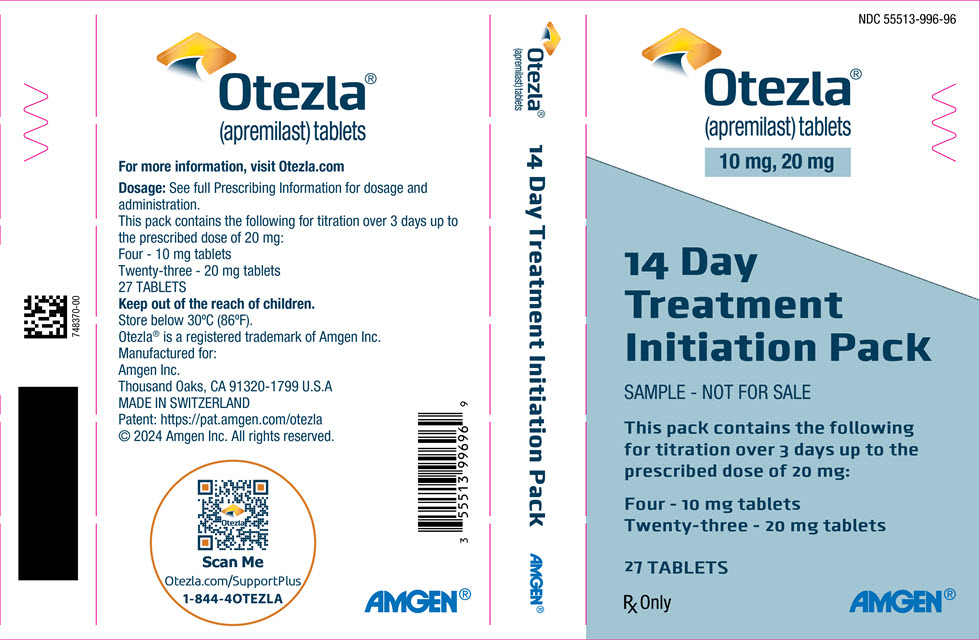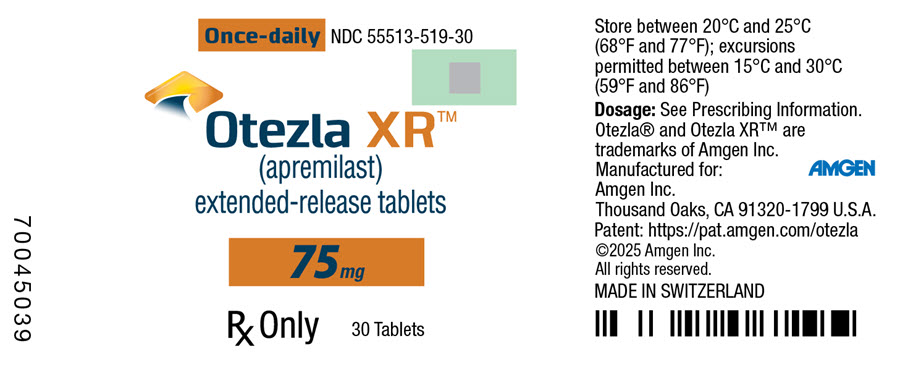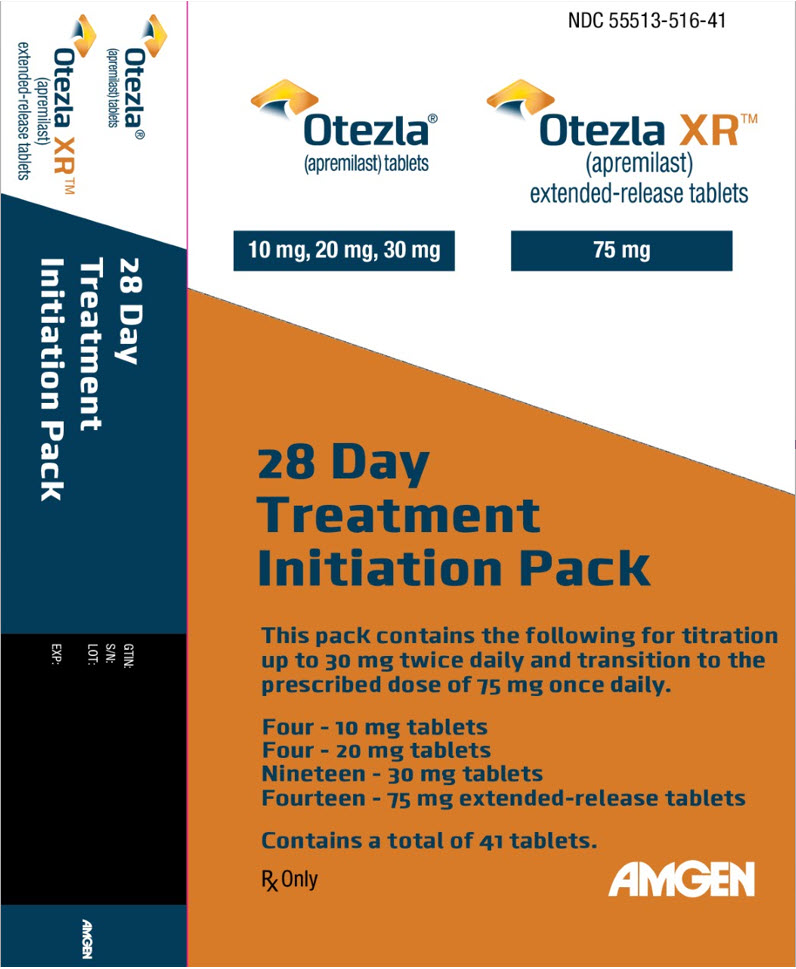 DRUG LABEL: Otezla
NDC: 55513-137 | Form: TABLET, FILM COATED
Manufacturer: Amgen, Inc
Category: prescription | Type: HUMAN PRESCRIPTION DRUG LABEL
Date: 20251223

ACTIVE INGREDIENTS: APREMILAST 30 mg/1 1
INACTIVE INGREDIENTS: MICROCRYSTALLINE CELLULOSE; CROSCARMELLOSE SODIUM; MAGNESIUM STEARATE; POLYVINYL ALCOHOL, UNSPECIFIED; TITANIUM DIOXIDE; POLYETHYLENE GLYCOL, UNSPECIFIED; TALC; FERRIC OXIDE RED; FERRIC OXIDE YELLOW; FERROSOFERRIC OXIDE

HIGHLIGHTS OF PRESCRIBING INFORMATION

These highlights do not include all the information needed to use OTEZLA/OTEZLA XR safely and effectively. See full prescribing information for OTEZLA/OTEZLA XR.
OTEZLA® (apremilast) tablets, for oral use
OTEZLA XR™ (apremilast) extended-release tablets, for oral use
Initial U.S. Approval: 2014

RECENT MAJOR CHANGES

Indications and Usage (1) | 08/2025
Dosage and Administration (2) | 08/2025

1 INDICATIONS AND USAGE

OTEZLA/OTEZLA XR, an inhibitor of phosphodiesterase 4 (PDE4), is indicated for the treatment of:

Adult patients with:

- Active psoriatic arthritis (1.1)
- Plaque psoriasis who are candidates for phototherapy or systemic therapy (1.2)
- Oral ulcers associated with Behçet's Disease (1.3)

Pediatric patients 6 years of age and older with:

- Active psoriatic arthritis (1.1)
- Moderate to severe plaque psoriasis who are candidates for phototherapy or systemic therapy (1.2)

In the pediatric population, OTEZLA is indicated for patients weighing at least 20 kg, and OTEZLA XR is indicated for patients weighing at least 50 kg.

2 DOSAGE AND ADMINISTRATION

To reduce the risk of gastrointestinal symptoms, titrate to recommended dosage as follows:

- Adults with Psoriatic Arthritis, Plaque Psoriasis, or Behçet's Disease
  - See Table 1 for the initial titration schedule. Recommended maintenance dosage is OTEZLA 30 mg twice daily or OTEZLA XR 75 mg once daily (2.1)
- Pediatric Patients 6 Years of Age and Older and Weighing at Least 20 kg with Psoriatic Arthritis or Moderate to Severe Plaque Psoriasis
  - See Table 2 for the initial titration schedule (2.1)
    - For patients weighing 50 kg or more: Recommended maintenance dosage is OTEZLA 30 mg twice daily or OTEZLA XR 75 mg once daily (2.1)
    - For patients weighing 20 kg to less than 50 kg: Recommended maintenance dosage is OTEZLA 20 mg twice daily (2.1)
- Dosage in Patients with Severe Renal Impairment:
  - Adult Patients: For initial dosage titration, titrate using only morning schedule listed in Table 1 and skip afternoon doses. Recommended maintenance dosage is OTEZLA 30 mg once daily (2.3)
  - Pediatric Patients 6 Years of Age and Older and Weighing at Least 20 kg with Psoriatic Arthritis or Moderate to Severe Plaque Psoriasis: For initial dosage titration, titrate using only morning schedule for appropriate body weight category in Table 2 and skip afternoon doses (2.3)
    - For patients weighing 50 kg or more: Recommended maintenance dosage is OTEZLA 30 mg once daily (2.3)
    - For patients weighing 20 kg to less than 50 kg: Recommended maintenance dosage is OTEZLA 20 mg once daily (2.3)

3 DOSAGE FORMS AND STRENGTHS

OTEZLA Tablets: 10 mg, 20 mg, 30 mg (3)

OTEZLA XR Tablets: 75 mg (3)

4 CONTRAINDICATIONS

Known hypersensitivity to apremilast or to any of the excipients in the formulation (4)

5 WARNINGS AND PRECAUTIONS

- Hypersensitivity: Cases of angioedema and anaphylaxis have been reported during post marketing surveillance. Avoid the use of OTEZLA/OTEZLA XR in patients with known hypersensitivity to apremilast or to any of the excipients in the formulation. If signs or symptoms of serious hypersensitivity reactions develop during treatment, discontinue OTEZLA/OTEZLA XR and institute appropriate therapy (5.1)
- Diarrhea, Nausea, and Vomiting: Consider OTEZLA/OTEZLA XR dosage reduction or suspension if patients develop severe diarrhea, nausea, or vomiting (5.2)
- Depression: Advise patients, their caregivers, and families to be alert for the emergence or worsening of depression, suicidal thoughts or other mood changes and if such changes occur to contact their healthcare provider. Carefully weigh risks and benefits of treatment with OTEZLA/OTEZLA XR in patients with a history of depression and/or suicidal thoughts or behavior (5.3)
- Weight Decrease: Monitor weight regularly. If unexplained or clinically significant weight loss occurs, evaluate weight loss and consider discontinuation of OTEZLA/OTEZLA XR (5.4)
- Drug Interactions: Use with strong cytochrome P450 enzyme inducers (e.g., rifampin, phenobarbital, carbamazepine, phenytoin) is not recommended because loss of efficacy may occur (5.5, 7.1)

6 ADVERSE REACTIONS

- Psoriatic Arthritis: The most common adverse reactions (≥ 5%) are diarrhea, nausea, and headache (6.1)
- Plaque Psoriasis: The most common adverse reactions (≥ 5%) are diarrhea, nausea, upper respiratory tract infection, and headache, including tension headache (6.1)
- Behçet's Disease: The most common adverse reactions (≥ 10%) are diarrhea, nausea, headache, and upper respiratory tract infection (6.1)

To report SUSPECTED ADVERSE REACTIONS, contact Amgen Inc. at 1-800-77-AMGEN (1-800-772-6436) or FDA at 1-800-FDA-1088 or www.fda.gov/medwatch.

8 USE IN SPECIFIC POPULATIONS

Severe Renal Impairment: Increased systemic exposure of OTEZLA has been observed. For adults and for pediatric patients weighing 50 kg or more, reduce dosage to OTEZLA 30 mg once daily. For pediatric patients weighing 20 kg to less than 50 kg, reduce dosage to OTEZLA 20 mg once daily (2.3, 8.6).

FULL PRESCRIBING INFORMATION

1 INDICATIONS AND USAGE

1.1 Psoriatic Arthritis

OTEZLA is indicated for the treatment of adult patients and pediatric patients 6 years of age and older and weighing at least 20 kg with active psoriatic arthritis.

OTEZLA XR is indicated for the treatment of adult patients and pediatric patients 6 years of age and older and weighing at least 50 kg with active psoriatic arthritis.

1.2 Plaque Psoriasis

OTEZLA/OTEZLA XR is indicated for the treatment of adult patients with plaque psoriasis who are candidates for phototherapy or systemic therapy.

OTEZLA is indicated for the treatment of pediatric patients 6 years of age and older and weighing at least 20 kg with moderate to severe plaque psoriasis who are candidates for phototherapy or systemic therapy.

OTEZLA XR is indicated for the treatment of pediatric patients 6 years of age and older and weighing at least 50 kg with moderate to severe plaque psoriasis who are candidates for phototherapy or systemic therapy.

1.3 Oral Ulcers Associated with Behçet's Disease

OTEZLA/OTEZLA XR is indicated for the treatment of adult patients with oral ulcers associated with Behçet's Disease.

2 DOSAGE AND ADMINISTRATION

2.1 Recommended Dosage in Adult and Pediatric Patients with Psoriatic Arthritis, Plaque Psoriasis, and Behçet's Disease

Adult Patients with Psoriatic Arthritis, Plaque Psoriasis, or Behçet's Disease

The recommended initial dosage titration from Day 1 to Day 5 is shown in Table 1. Following the 5-day titration with OTEZLA, the recommended maintenance dosage is OTEZLA 30 mg twice daily or OTEZLA XR 75 mg once daily taken orally starting on Day 6. This titration is intended to reduce the gastrointestinal symptoms associated with initial therapy.

Table 1. Dosage Titration Schedule for Adult Patients with Psoriatic Arthritis, Plaque Psoriasis, or Behçet's Disease
OTEZLA Dosage Titration [OTEZLA tablets should be used for the initial titration regardless of whether OTEZLA or OTEZLA XR will be used for the maintenance dosage.] |  |  |  |  |  |  |  |  | OTEZLA/OTEZLA XR Maintenance Dosage
Day 1 | Day 2 |  | Day 3 |  | Day 4 |  | Day 5 |  | Day 6 & thereafter
AM | AM | PM | AM | PM | AM | PM | AM | PM
10 mg | 10 mg | 10 mg | 10 mg | 20 mg | 20 mg | 20 mg | 20 mg | 30 mg | OTEZLA 30 mg BID OR OTEZLA XR 75 mg QD
BID = twice daily; QD = once daily

Pediatric Patients 6 Years of Age and Older and Weighing at Least 20 kg with Psoriatic Arthritis Moderate to Severe Plaque Psoriasis

The recommended dosage for pediatric patients 6 years of age and older and weighing at least 20 kg with psoriatic arthritis or moderate to severe plaque psoriasis is based on body weight. Following the appropriate initial titration schedule shown in Table 2, the recommended maintenance dosage is:

- For pediatric patients who weigh at least 50 kg: OTEZLA 30 mg twice daily or OTEZLA XR 75 mg once daily taken orally
- For pediatric patients who weigh from 20 kg to less than 50 kg: OTEZLA 20 mg twice daily taken orally

The initial titration is intended to reduce the gastrointestinal symptoms associated with initial therapy.

Table 2. Dosage Titration Schedule for Pediatric Patients 6 Years of Age and Older and Weighing at Least 20 kg with Psoriatic Arthritis or Moderate to Severe Plaque Psoriasis
 | OTEZLA Dosage Titration [OTEZLA tablets should be used for the initial titration regardless of whether OTEZLA or OTEZLA XR will be used for the maintenance dosage.] |  |  |  |  |  |  |  |  | OTEZLA/OTEZLA XR Maintenance Dosage
Body Weight | Day 1 | Day 2 |  | Day 3 |  | Day 4 |  | Day 5 |  | Day 6 & thereafter
 | AM | AM | PM | AM | PM | AM | PM | AM | PM
50 kg or more | 10 mg | 10 mg | 10 mg | 10 mg | 20 mg | 20 mg | 20 mg | 20 mg | 30 mg | OTEZLA 30 mg BID OR OTEZLA XR 75 mg QD
20 kg to less than 50 kg | 10 mg | 10 mg | 10 mg | 10 mg | 20 mg | 20 mg | 20 mg | 20 mg | 20 mg | OTEZLA 20 mg BID
BID = twice daily; QD = once daily

2.2 Switching Between OTEZLA and OTEZLA XR

Patients treated with OTEZLA 30 mg twice daily may be switched to OTEZLA XR 75 mg once daily the day following the last dose of OTEZLA 30 mg.

Patients treated with OTEZLA XR 75 mg once daily may be switched to OTEZLA 30 mg twice daily the day following the last dose of OTEZLA XR 75 mg.

2.3 Dosage Adjustment in Adult and Pediatric Patients with Severe Renal Impairment

Adult Patients with Psoriatic Arthritis, Plaque Psoriasis, or Behçet's Disease

For initial dosage titration in adult patients with severe renal impairment (creatinine clearance [CLcr] of less than 30 mL per minute estimated by the Cockcroft–Gault equation), titrate OTEZLA using only the AM schedule listed in Table 1 and skip the PM doses. The recommended maintenance dosage in this group is OTEZLA 30 mg once daily [see Use in Specific Populations (8.6) and Clinical Pharmacology (12.3)].

OTEZLA XR is not recommended for adult patients with severe renal impairment; the appropriate dosage for these patients has not been determined [see Use in Specific Populations (8.6) and Clinical Pharmacology (12.3)].

Pediatric Patients 6 Years of Age and Older and Weighing at Least 20 kg with Psoriatic Arthritis or Moderate to Severe Plaque Psoriasis

For initial dosage titration in pediatric patients 6 years of age and older and weighing at least 20 kg with psoriatic arthritis or moderate to severe plaque psoriasis and severe renal impairment (CLcr of less than 30 mL per minute estimated by the Cockcroft–Gault equation), titrate OTEZLA using only the AM schedule listed in Table 2 for the appropriate body weight category and skip the PM doses. The recommended maintenance dosage is:

- For pediatric patients who weigh at least 50 kg: OTEZLA 30 mg once daily taken orally
- For pediatric patients who weigh 20 kg to less than 50 kg: OTEZLA 20 mg once daily taken orally

OTEZLA XR is not recommended for pediatric patients with severe renal impairment; the appropriate dosage for these patients has not been determined [see Use in Specific Populations (8.6) and Clinical Pharmacology (12.3)].

2.4 Important Administration Instructions

- Administer OTEZLA/OTEZLA XR with or without food.
- Swallow tablets whole. Do not crush, split, or chew.

3 DOSAGE FORMS AND STRENGTHS

OTEZLA is available as diamond-shaped, film-coated tablets in the following dosage strengths:

- 10-mg pink tablet engraved with "APR" on one side and "10" on the other side
- 20-mg brown tablet engraved with "APR" on one side and "20" on the other side
- 30-mg beige tablet engraved with "APR" on one side and "30" on the other side

OTEZLA XR is available as 75 mg round, biconvex, pink, film-coated extended-release tablets with "APR 75" printed in black on one side and a hole or indentation on either side of the tablet, which may or may not be visible.

4 CONTRAINDICATIONS

OTEZLA/OTEZLA XR is contraindicated in patients with a known hypersensitivity to apremilast or to any of the excipients in the formulation [see Warnings and Precautions (5.1), see Adverse Reactions (6.1)].

5 WARNINGS AND PRECAUTIONS

5.1 Hypersensitivity

Hypersensitivity reactions, including cases of angioedema and anaphylaxis, have been reported during post marketing surveillance. Avoid the use of OTEZLA/OTEZLA XR in patients with known hypersensitivity to apremilast or to any of the excipients in the formulation. If signs or symptoms of serious hypersensitivity reactions develop during treatment, discontinue OTEZLA/OTEZLA XR and institute appropriate therapy.

5.2 Diarrhea, Nausea, and Vomiting

There have been reports of severe diarrhea, nausea, and vomiting associated with the use of OTEZLA. Most events occurred within the first few weeks of treatment. In some cases, patients were hospitalized. Patients 65 years of age or older and patients taking medications that can lead to volume depletion or hypotension may be at a higher risk of complications from severe diarrhea, nausea, or vomiting. Monitor patients who are more susceptible to complications of diarrhea or vomiting. Patients who reduced dosage or discontinued OTEZLA generally improved quickly. Consider OTEZLA/OTEZLA XR dosage reduction or suspension if patients develop severe diarrhea, nausea, or vomiting.

5.3 Depression

Treatment with apremilast is associated with an increased incidence of depression. Before using OTEZLA/OTEZLA XR in patients with a history of depression and/or suicidal thoughts or behavior, carefully weigh the risks and benefits of treatment with OTEZLA/OTEZLA XR. Advise patients, their caregivers, and families of the need to be alert for the emergence or worsening of depression, suicidal thoughts or other mood changes, and if such changes occur to contact their healthcare provider. Carefully evaluate the risks and benefits of continuing treatment with OTEZLA/OTEZLA XR if such events occur.

Psoriatic Arthritis: During the 16-week placebo-controlled period of the 3 controlled clinical trials, 1.0% (10/998) of subjects treated with OTEZLA reported depression or depressed mood compared to 0.8% (4/495) treated with placebo. During the clinical trials, 0.3% (4/1441) of subjects treated with OTEZLA discontinued treatment due to depression or depressed mood compared with none in placebo treated subjects (0/495). Depression was reported as serious in 0.2% (3/1441) of subjects exposed to OTEZLA, compared to none in placebo-treated subjects (0/495). Instances of suicidal ideation and behavior have been observed in 0.2% (3/1441) of subjects while receiving OTEZLA, compared to none in placebo treated subjects (0/495). In the clinical trials, 2 subjects who received placebo committed suicide compared to none in OTEZLA-treated subjects.

Plaque Psoriasis: During the 16-week placebo-controlled period of the 3 controlled clinical trials in adult subjects with moderate to severe plaque psoriasis, 1.3% (12/920) of subjects treated with OTEZLA reported depression compared to 0.4% (2/506) treated with placebo. During the clinical trials, 0.1% (1/1308) of subjects treated with OTEZLA discontinued treatment due to depression compared with none in placebo-treated subjects (0/506). Depression was reported as serious in 0.1% (1/1308) of subjects exposed to OTEZLA, compared to none in placebo-treated subjects (0/506). Instances of suicidal behavior have been observed in 0.1% (1/1308) of subjects while receiving OTEZLA, compared to 0.2% (1/506) in placebo-treated subjects. In the clinical trials, one subject treated with OTEZLA attempted suicide while one who received placebo committed suicide.

During the 16-week placebo-controlled period of the clinical trial in adults with mild to moderate plaque psoriasis, the incidence of subjects reporting depression was similar to what was observed in the adult moderate to severe plaque psoriasis trials.

Behçet's Disease: During the placebo-controlled period of the phase 3 trial, 1% (1/104) of subjects treated with OTEZLA reported depression/depressed mood compared to 1% (1/103) treated with placebo. None of these reports of depression was serious or led to discontinuation from the trial. No instances of suicidal ideation or behavior were reported during the placebo-controlled period of the phase 3 trial in subjects treated with OTEZLA (0/104) or treated with placebo (0/103).

5.4 Weight Decrease

Weight loss may occur in adult or pediatric patients treated with OTEZLA/OTEZLA XR.

Regularly monitor the weight of patients treated with OTEZLA/OTEZLA XR. If unexplained or clinically significant weight loss occurs, evaluate weight loss and consider discontinuation of OTEZLA/OTEZLA XR [see Adverse Reactions (6.1)].

Weight Loss in Adult Patients

During the placebo-controlled period of the trials in psoriatic arthritis (PsA), weight decrease between 5%-10% of body weight was reported in 10% (49/497) of subjects treated with OTEZLA 30 mg twice daily compared to 3.3% (16/495) treated with placebo.

During the placebo-controlled period of the trials in adults with moderate to severe plaque psoriasis, weight decrease between 5%-10% of body weight occurred in 12% (96/784) of subjects treated with OTEZLA compared to 5% (19/382) treated with placebo. Weight decrease of ≥ 10% of body weight occurred in 2% (16/784) of subjects treated with OTEZLA 30 mg twice daily compared to 1% (3/382) subjects treated with placebo.

During the placebo-controlled period of the clinical trial in adults with mild to moderate plaque psoriasis, weight decrease was similar to what was observed in the trials of adults with moderate to severe plaque psoriasis.

During the placebo-controlled period of the phase 3 trial in Behçet's Disease, weight decrease > 5% of body weight was reported in 4.9% (5/103) of subjects treated with OTEZLA 30 mg twice daily compared to 3.9% (4/102) subjects treated with placebo.

Weight Loss in Pediatric Patients

During the placebo-controlled period of the clinical trial in pediatric subjects 6 years of age and older with moderate to severe plaque psoriasis, weight decrease between 5%-10% of body weight occurred in 12% (19/163) of pediatric subjects treated with OTEZLA compared to 2.5% (2/80) of pediatric subjects treated with placebo. Weight decrease of ≥ 10% of body weight occurred in 1% (1/163) of pediatric subjects treated with OTEZLA twice daily compared to 0% (0/80) of pediatric subjects treated with placebo.

Closely monitor growth (height and weight) in pediatric patients treated with OTEZLA/OTEZLA XR. Pediatric patients who are not growing or gaining weight as expected may need to have their treatment interrupted.

5.5 Drug Interactions

Co-administration of strong cytochrome P450 enzyme inducer, rifampin, resulted in a reduction of systemic exposure of apremilast, which may result in a loss of efficacy of OTEZLA/OTEZLA XR. Therefore, the use of cytochrome P450 enzyme inducers (e.g., rifampin, phenobarbital, carbamazepine, phenytoin) with OTEZLA/OTEZLA XR is not recommended [see Drug Interactions (7.1) and Clinical Pharmacology (12.3)].

6 ADVERSE REACTIONS

The following adverse reactions are described elsewhere in the labeling:

- Hypersensitivity [see Warnings and Precautions (5.1)]
- Diarrhea, Nausea, and Vomiting [see Warnings and Precautions (5.2)]
- Depression [see Warnings and Precautions (5.3)]
- Weight Decrease [see Warnings and Precautions (5.4)]
- Drug Interactions [see Warnings and Precautions (5.5)]

6.1 Clinical Trials Experience

Because clinical trials are conducted under widely varying conditions, adverse reaction rates observed in the clinical trials of a drug cannot be directly compared to rates in the clinical trials of another drug and may not reflect the rates observed in clinical practice.

Psoriatic Arthritis Clinical Trials

OTEZLA was evaluated in three multicenter, randomized, double-blind, placebo-controlled trials (PsA-1, PsA-2, and PsA-3) of similar design in adult subjects with active psoriatic arthritis [see Clinical Studies (14.1)]. Across the three trials, there were 1493 subjects randomized equally to placebo, OTEZLA 20 mg twice daily or OTEZLA 30 mg twice daily. Titration was used over the first 5 days [see Dosage and Administration (2.1)]. Placebo subjects whose tender and swollen joint counts had not improved by at least 20% were re-randomized 1:1 in a blinded fashion to either OTEZLA 20 mg twice daily or 30 mg twice daily at week 16 while OTEZLA subjects remained on their initial treatment. Subjects ranged in age from 18 to 83 years, with an overall median age of 51 years.

The majority of the most common adverse reactions presented in Table 3 occurred within the first 2 weeks of treatment and tended to resolve over time with continued dosing. Diarrhea, headache, and nausea were the most commonly reported adverse reactions. The most common adverse reactions leading to discontinuation for subjects taking OTEZLA were nausea (1.8%), diarrhea (1.8%), and headache (1.2%). The proportion of subjects with psoriatic arthritis who discontinued treatment due to any adverse reaction was 4.6% for subjects taking OTEZLA 30 mg twice daily and 1.2% for placebo-treated subjects.

Table 3. Adverse Reactions Reported in ≥ 2% of Adult Subjects with Active Psoriatic Arthritis on OTEZLA 30 mg Twice Daily and ≥ 1% than That Observed in Subjects on Placebo up to Day 112 (Week 16)
 | Placebo |  | OTEZLA 30 mg BID [BID = twice daily.]
Adverse Reactions | Day 1 to 5 (N = 495) n (%) [n (%) indicates number of subjects and percent.] | Day 6 to Day 112 (N = 490) n (%) | Day 1 to 5 (N = 497) n (%) | Day 6 to Day 112 (N = 493) n (%)
Diarrhea [Of the reported gastrointestinal adverse reactions, 1 subject experienced a serious adverse reaction of nausea and vomiting in OTEZLA 30 mg twice daily; 1 subject treated with OTEZLA 20 mg twice daily experienced a serious adverse reaction of diarrhea; 1 subject treated with OTEZLA 30 mg twice daily experienced a serious adverse reaction of headache.] | 6 (1.2) | 8 (1.6) | 46 (9.3) | 38 (7.7)
Nausea | 7 (1.4) | 15 (3.1) | 37 (7.4) | 44 (8.9)
Headache | 9 (1.8) | 11 (2.2) | 24 (4.8) | 29 (5.9)
Upper respiratory tract infection [Of the reported adverse drug reactions none were serious.] | 3 (0.6) | 9 (1.8) | 3 (0.6) | 19 (3.9)
Vomiting | 2 (0.4) | 2 (0.4) | 4 (0.8) | 16 (3.2)
Nasopharyngitis | 1 (0.2) | 8 (1.6) | 1 (0.2) | 13 (2.6)
Abdominal pain upper | 0 (0.0) | 1 (0.2) | 3 (0.6) | 10 (2.0)

Moderate to Severe Plaque Psoriasis Clinical Trials

Adverse Reactions from Clinical Trials in Adults

The safety of OTEZLA was assessed in 1426 subjects in three randomized, double-blind, placebo-controlled trials in adult subjects with moderate to severe plaque psoriasis who were candidates for phototherapy or systemic therapy. Subjects were randomized to receive OTEZLA 30 mg twice daily or placebo twice daily. Titration was used over the first 5 days [see Dosage and Administration (2.1)]. Subjects ranged in age from 18 to 83 years, with an overall median age of 46 years.

Diarrhea, nausea, and upper respiratory tract infection were the most commonly reported adverse reactions (see Table 4). The most common adverse reactions leading to discontinuation for subjects taking OTEZLA were nausea (1.6%), diarrhea (1.0%), and headache (0.8%). The proportion of subjects with plaque psoriasis who discontinued treatment due to any adverse reaction was 6.1% for subjects treated with OTEZLA 30 mg twice daily and 4.1% for placebo-treated subjects.

Table 4. Adverse Reactions Reported in ≥ 1% of Adult Subjects with Moderate to Severe Plaque Psoriasis on OTEZLA and With Greater Frequency Than in Subjects on Placebo up to Day 112 (Week 16)
Adverse Reactions | Placebo (N = 506) n (%) | OTEZLA 30 mg BID [BID = twice daily.] (N = 920) n (%)
Diarrhea | 32 (6) | 160 (17)
Nausea | 35 (7) | 155 (17)
Upper respiratory tract infection | 31 (6) | 84 (9)
Tension headache | 21 (4) | 75 (8)
Headache | 19 (4) | 55 (6)
Abdominal pain [Two subjects treated with OTEZLA experienced serious adverse reaction of abdominal pain.] | 11 (2) | 39 (4)
Vomiting | 8 (2) | 35 (4)
Fatigue | 9 (2) | 29 (3)
Dyspepsia | 6 (1) | 29 (3)
Decreased appetite | 5 (1) | 26 (3)
Insomnia | 4 (1) | 21 (2)
Back pain | 4 (1) | 20 (2)
Migraine | 5 (1) | 19 (2)
Frequent bowel movements | 1 (0) | 17 (2)
Depression | 2 (0) | 12 (1)
Bronchitis | 2 (0) | 12 (1)
Tooth abscess | 0 (0) | 10 (1)
Folliculitis | 0 (0) | 9 (1)
Sinus headache | 0 (0) | 9 (1)

Severe worsening of psoriasis (rebound) occurred in 0.3% (4/1184) subjects following discontinuation of treatment with OTEZLA.

OTEZLA was evaluated in a Phase 3, multicenter, randomized, placebo-controlled trial (PSOR-3) in adults with moderate to severe plaque psoriasis of the scalp [see Clinical Studies (14.2)]. A total of 302 subjects were randomized to receive OTEZLA 30 mg twice daily or placebo twice daily. The most commonly reported adverse reactions that occurred at a higher rate in the OTEZLA group than in the placebo group were: diarrhea (31% vs. 11%), nausea (22% vs. 6%), headache (12% vs. 5%), and vomiting (6% vs. 2%). The proportion of subjects who discontinued treatment because of any adverse reaction during the 16-week placebo-controlled period of the trial was 6% for subjects who received OTEZLA 30 mg twice daily and 3% for subjects who received placebo. Gastrointestinal adverse reactions that led to discontinuation of treatment were diarrhea (3% vs. 0%), nausea (1.5% vs. 1%), and vomiting (1.5% vs. 0%) in the OTEZLA group compared to placebo.

OTEZLA was evaluated in a Phase 3, multicenter, randomized, placebo-controlled trial (PSOR-5) in adults with moderate to severe plaque psoriasis of the genital area [see Clinical Studies (14.2)]. A total of 289 subjects were randomized to receive OTEZLA 30 mg twice daily or placebo twice daily. Overall, the safety profile observed in the OTEZLA group during the placebo-controlled phase was consistent with the safety profile previously established in adult subjects with moderate to severe plaque psoriasis.

Adverse Reactions from Clinical Trials in Pediatric Subjects 6 to 17 Years of Age

OTEZLA was evaluated in a Phase 3, multicenter, randomized, placebo-controlled trial (PSOR-6) in pediatric subjects 6 to 17 years of age with moderate to severe plaque psoriasis [see Clinical Studies (14.3)]. A total of 245 subjects were randomized to receive OTEZLA (163 subjects, at a dosage of 20 mg twice daily or 30 mg twice daily, based on body weight) or placebo (82 subjects) twice daily during the 16-week placebo-controlled phase of the trial. The trial also included a 36-week extension phase during which all subjects received OTEZLA 20 mg or 30 mg twice daily. Overall, the safety profile observed in pediatric subjects treated with OTEZLA during the study was consistent with the safety profile established in adult subjects with moderate to severe plaque psoriasis.

Mild to Moderate Plaque Psoriasis Clinical Trial in Adults

OTEZLA was evaluated in a Phase 3, multicenter, randomized, placebo-controlled trial (PSOR-4) in adult subjects with mild to moderate plaque psoriasis [see Clinical Studies (14.4)]. A total of 595 subjects were randomized to receive OTEZLA 30 mg twice daily (297 subjects) or placebo twice daily (298 subjects) during the placebo-controlled phase of the trial. The trial also included an open label extension phase during which all subjects received OTEZLA 30 mg twice daily. Overall, the safety profile observed in the OTEZLA group during the placebo-controlled phase was consistent with the safety profile previously established in adult subjects with moderate to severe plaque psoriasis.

Behçet's Disease Clinical Trials

OTEZLA was evaluated in a Phase 3, multicenter, randomized, placebo-controlled trial (BCT-002) in adult subjects with Behçet's Disease (BD) with active oral ulcers [see Clinical Studies (14.5)]. A total of 207 subjects were randomized to receive OTEZLA 30 mg twice daily or placebo twice daily. Titration was used over the first 5 days [see Dosage and Administration (2.1)]. After Week 12, all subjects received treatment with OTEZLA 30 mg twice daily. Subjects ranged in age from 19 to 72, with a mean age of 40 years.

Diarrhea, nausea, headache, and upper respiratory tract infection were the most commonly reported adverse reactions (see Table 5). The proportion of subjects with BD who discontinued treatment due to any adverse reaction during the placebo-controlled period of the trial, was 2.9% for subjects treated with OTEZLA 30 mg twice daily and 4.9% for placebo-treated subjects.

Table 5. Adverse Reactions Reported in ≥ 5% of Adult Subjects with BD with Active Oral Ulcers on OTEZLA and with at Least 1% Greater Frequency than Subjects on Placebo up to Week 12
Adverse Reactions | Placebo (N = 103) n (%) | OTEZLA 30 mg twice daily (N = 104) n (%)
Diarrhea [There were no serious adverse reactions of diarrhea, nausea or vomiting.] | 21 (20.4) | 43 (41.3)
Nausea | 11 (10.7) | 20 (19.2)
Headache | 11 (10.7) | 15 (14.4)
Upper respiratory tract infection | 5 (4.9) | 12 (11.5)
Abdominal pain upper | 2 (1.9) | 9 (8.7)
Vomiting | 2 (1.9) | 9 (8.7)
Back pain | 6 (5.8) | 8 (7.7)
Viral upper respiratory tract infection | 5 (4.9) | 7 (6.7)
Arthralgia | 3 (2.9) | 6 (5.8)

Other adverse reactions reported in subjects on OTEZLA in psoriatic arthritis, plaque psoriasis, and Behçet's Disease clinical trials are:

- Gastrointestinal Disorders: Gastroesophageal reflux disease
- Immune System Disorders: Hypersensitivity
- Investigations: Weight decrease
- Metabolism and Nutrition Disorders: Decreased appetite [One subject treated with OTEZLA 30 mg twice daily experienced a serious adverse reaction.]
- Nervous System Disorders: Migraine
- Respiratory, Thoracic, and Mediastinal Disorders: Cough
- Skin and Subcutaneous Tissue Disorders: Rash

7 DRUG INTERACTIONS

7.1 Strong CYP450 Inducers

Co-administration with strong CYP450 inducers (such as rifampin) decreases apremilast exposure and may result in loss of efficacy of OTEZLA/OTEZLA XR [see Warnings and Precautions (5.5) and Clinical Pharmacology (12.3)].

8 USE IN SPECIFIC POPULATIONS

8.1 Pregnancy

Risk Summary

Available data with OTEZLA use in pregnant women have not identified a drug-associated risk of major birth defects or adverse maternal or fetal outcomes (see Data).

In animal embryo-fetal development studies, the administration of apremilast to pregnant cynomolgus monkeys during organogenesis resulted in dose-related increases in abortion/embryo-fetal death at dose exposures approximately 2-times the maximum recommended human therapeutic dose (MRHD) and no adverse effect at an exposure of 1.4-times the MRHD. When apremilast was administered to pregnant mice during organogenesis, there were no apremilast-induced malformations up to exposures 4-times the MRHD. Based on findings from animal reproduction studies, OTEZLA/OTEZLA XR may increase the risk for fetal loss (see Data). Advise pregnant women of the potential risk of fetal loss.

The background risk of major birth defects and miscarriage for the indicated populations is unknown. All pregnancies have a background risk of birth defect, loss, or other adverse outcomes. In the U.S. general population, the estimated background risk of major birth defects and miscarriage in clinically recognized pregnancies is 2% to 4% and 15% to 20%, respectively.

Data

Human Data

A pregnancy registry conducted by the Organization of Teratology Information Specialists (OTIS) in the United States and Canada assessed the risk of major birth defects in liveborn infants of women with psoriatic arthritis, psoriasis, or Behçet's Disease exposed to apremilast in the first trimester. The study compared pregnant women treated with apremilast (n = 15) with disease matched pregnant women who were not exposed to apremilast (n = 106). In the apremilast-exposed cohort, there were no reports of liveborn infants with major birth defects nor miscarriages. One stillbirth was reported in the apremilast exposed cohort. These data are limited by the small sample size of apremilast-exposed pregnancies.

Animal Data

In an embryo-fetal developmental study, pregnant cynomolgus monkeys were administered apremilast at doses of 20, 50, 200, or 1000 mg/kg/day during the period of organogenesis (gestation Days [GD] 20 through 50). There was a dose -related increase in spontaneous abortions, with most abortions occurring during Weeks 3 to 4 of dosing in the first trimester, at doses approximately 2-times the MRHD and greater (on an area under the curve [AUC] basis at doses ≥ 50 mg/kg/day). No abortifacient effects were observed at a dose approximately 1.4-times the MRHD (on an AUC basis at a dose of 20 mg/kg/day). Although there was no evidence for a teratogenic effect at doses of 20 mg/kg/day and greater when examined at Day 100, aborted fetuses were not examined.

In an embryo-fetal development study in mice, apremilast was administered at doses of 250, 500, or 750 mg/kg/day to dams during organogenesis (GD 6 through 15). In a combined fertility and embryo-fetal development study in mice, apremilast was administered at doses of 10, 20, 40, or 80 mg/kg/day starting 15 days before cohabitation and continuing through GD 15. No teratogenic findings attributed to apremilast were observed in either study; however, there was an increase in post-implantation loss at doses corresponding to a systemic exposure of approximately 2-times the MRHD and greater (≥ 20 mg/kg/day). At doses of ≥ 20 mg/kg/day skeletal variations included incomplete ossification sites of tarsals, skull, sternebra, and vertebrae. No effects were observed at a dose approximately 1.3-times the MRHD (10 mg/kg/day).

Apremilast distributed across the placenta into the fetal compartment in mice and monkeys.

In a pre and postnatal study in mice, apremilast was administered to pregnant female mice at doses of 10, 80, or 300 mg/kg/day from Day 6 of gestation through Day 20 of lactation, with weaning on Day 21. Dystocia, reduced viability, and reduced birth weights occurred at doses corresponding to ≥ 4-times the MRHD (on an AUC basis at doses ≥ 80 mg/kg/day). No adverse effects occurred at a dose 1.3-times the MRHD (10 mg/kg/day). There was no evidence for functional impairment of physical development, behavior, learning ability, immune competence, or fertility in the offspring at doses up to 7.5-times the MRHD (on an AUC basis at a dose of 300 mg/kg/day).

8.2 Lactation

Risk Summary

There are no data on the presence of apremilast in human milk, its effects on the breastfed infant, or its effects on milk production. However, apremilast was detected in the milk of lactating mice (see Data). When a drug is present in animal milk, it is likely that the drug will be present in human milk. The developmental and health benefits of breastfeeding should be considered along with the mother's clinical need for OTEZLA/OTEZLA XR and any potential adverse effects on the breastfed infant from OTEZLA/OTEZLA XR or from the underlying maternal condition.

Data

In mice, following a single oral administration of 10 mg/kg to dams on postpartum Day 13, apremilast concentrations in milk were approximately 1.5-times that of simultaneously collected blood samples.

8.4 Pediatric Use

OTEZLA

Plaque Psoriasis

The safety and effectiveness of OTEZLA have been established in pediatric patients 6 years of age and older and weighing at least 20 kg with moderate to severe plaque psoriasis who are candidates for phototherapy or systemic therapy. Use of OTEZLA in these patients is supported by evidence from a 52-week adequate and well-controlled clinical trial (PSOR-6) in 245 pediatric subjects 6 years of age and older with moderate to severe plaque psoriasis. Weight loss in OTEZLA-treated pediatric subjects was comparable to weight loss observed in adults [see Warnings and Precautions (5.4), Adverse Reactions (6.1) and Clinical Studies (14.3)].

Closely monitor growth (height and weight) in pediatric patients treated with OTEZLA. Pediatric patients who are not growing or gaining weight as expected may need to have their treatment interrupted.

The safety and effectiveness of OTEZLA have not been established in pediatric patients below the age of 6 years or weighing less than 20 kg with moderate to severe plaque psoriasis.

Psoriatic Arthritis

The safety and effectiveness of OTEZLA have been established for pediatric patients 6 years of age and older and weighing at least 20 kg with psoriatic arthritis. Use of OTEZLA in these patients is supported by evidence from adequate and well controlled trials of OTEZLA in adults with psoriatic arthritis, pharmacokinetic data from adult patients with psoriatic arthritis, adult patients with psoriasis, and pediatric patients with psoriasis, and safety data from a clinical trial in 245 pediatric patients 6 years of age and older with psoriasis. Steady-state exposure of OTEZLA in pediatric patients with psoriatic arthritis is estimated to be comparable to adults with psoriatic arthritis and pediatric patients with psoriasis [see Clinical Pharmacology (12.3)].

Closely monitor growth (height and weight) in OTEZLA-treated pediatric patients. Pediatric patients who are not growing or gaining weight as expected may need to have their treatment interrupted [see Warnings and Precautions (5.4)].

The safety and effectiveness of OTEZLA have not been established in pediatric patients below the age of 6 years or weighing less than 20 kg with psoriatic arthritis.

Behçet's Disease

The safety and effectiveness of OTEZLA have not been established in pediatric patients with psoriatic arthritis or oral ulcers associated with Behçet's Disease.

OTEZLA XR

Plaque Psoriasis and Psoriatic Arthritis

The safety and effectiveness of OTEZLA XR have been established for the treatment of moderate to severe plaque psoriasis and psoriatic arthritis in pediatric patients 6 years of age and older and weighing at least 50 kg. Use of OTEZLA XR in these patients is supported by pharmacokinetic data from healthy adults demonstrating comparable PK exposure between OTEZLA XR 75 mg once daily and OTEZLA 30 mg twice daily, which is the recommended OTEZLA dosage for pediatric patients weighing at least 50 kg [see Dosage and Administration (2.1), Clinical Pharmacology (12.3)].

Closely monitor growth (height and weight) in pediatric patients treated with OTEZLA XR. Pediatric patients who are not growing or gaining weight as expected may need to have their treatment interrupted.

The safety and effectiveness of OTEZLA XR have not been established in pediatric patients below the age of 6 years or weighing less than 50 kg with moderate to severe plaque psoriasis or psoriatic arthritis.

Behçet's Disease

The safety and effectiveness of OTEZLA XR have not been established in pediatric patients with oral ulcers associated with Behçet's Disease.

8.5 Geriatric Use

Of the 1493 patients who enrolled in Trials PsA-1, PsA-2, and PsA-3, a total of 146 (9.8%) psoriatic arthritis patients were 65 years of age and older, including 19 (1.3%) patients 75 years and older. No overall differences were observed in the safety profile of geriatric patients ≥ 65 years of age and younger adult patients < 65 years of age in the clinical trials.

Of the 1257 subjects who enrolled in two placebo-controlled plaque psoriasis trials (PSOR-1 and PSOR-2), a total of 108 (8.6%) plaque psoriasis patients were 65 years of age and older, including 9 (0.7%) patients who were 75 years of age and older. No overall differences were observed in the safety or effectiveness in geriatric patients ≥ 65 years of age and younger adult patients < 65 years of age in the clinical trials.

Because patients 65 years of age or older may be at a higher risk of complications such as volume depletion or hypotension from severe diarrhea, nausea, or vomiting, monitor geriatric patients closely for such complications [see Warnings and Precautions (5.2)].

8.6 Renal Impairment

OTEZLA pharmacokinetics were characterized in adult subjects with mild, moderate, and severe renal impairment as defined by a creatinine clearance of 60-89, 30-59, and less than 30 mL per minute, respectively, by the Cockcroft–Gault equation. No dosage adjustment is needed in patients with mild or moderate renal impairment. In adult patients with severe renal impairment, reduce the maintenance dosage to OTEZLA 30 mg once daily. In pediatric patients 6 years of age and older and weighing at least 20 kg with psoriatic arthritis or moderate to severe plaque psoriasis and severe renal impairment, reduce the maintenance dosage to OTEZLA 30 mg once daily for pediatric patients weighing at least 50 kg and to OTEZLA 20 mg once daily for pediatric patients weighing 20 kg to less than 50 kg [see Dosage and Administration (2.3) and Clinical Pharmacology (12.3)].

The pharmacokinetics of OTEZLA XR has not been evaluated in patients with renal impairment. In patients with severe renal impairment, it is recommended that OTEZLA be used instead of OTEZLA XR [see Dosage and Administration (2.3) and Clinical Pharmacology (12.3)].

8.7 Hepatic Impairment

Apremilast pharmacokinetics were characterized in subjects with moderate (Child Pugh B) and severe (Child Pugh C) hepatic impairment. No dosage adjustment is necessary in these patients.

11 DESCRIPTION

The active ingredient in OTEZLA/OTEZLA XR tablets is apremilast. Apremilast drug substance is non-hygroscopic. Apremilast drug substance is practically insoluble in water and slightly soluble in alcohol.

Apremilast is a phosphodiesterase 4 (PDE4) inhibitor. Apremilast is known chemically as
N-[2-[(1S)-1-(3-ethoxy-4-methoxyphenyl)-2-(methylsulfonyl)ethyl]-2,3-dihydro-1,3-dioxo-1H-isoindol-4-yl]acetamide. Its empirical formula is C22H24N2O7S and the molecular weight is 460.5.

The chemical structure is:

OTEZLA (apremilast) tablets are supplied in 10 mg, 20 mg, and 30 mg strengths for oral administration. Each tablet contains apremilast as the active ingredient and the following inactive ingredients: croscarmellose sodium, iron oxide red, iron oxide yellow (20 and 30 mg only), iron oxide black (30 mg only), lactose monohydrate, magnesium stearate, microcrystalline cellulose, polyethylene glycol, polyvinyl alcohol, talc, titanium dioxide.

OTEZLA XR (apremilast) extended-release tablets are supplied in a 75 mg strength for oral administration. Each tablet contains apremilast as the active ingredient and the following inactive ingredients: cellulose acetate, colloidal silicon dioxide, ferrosoferric oxide, hydroxypropyl methylcellulose acetate succinate, hypromellose, iron oxide red, magnesium stearate, mannitol, microcrystalline cellulose, polyethylene glycol, polyethylene oxide, sodium chloride, titanium dioxide.

12 CLINICAL PHARMACOLOGY

12.1 Mechanism of Action

Apremilast is an oral small molecule inhibitor of phosphodiesterase 4 (PDE4) specific for cyclic adenosine monophosphate (cAMP). PDE4 inhibition results in increased intracellular cAMP levels. The specific mechanism(s) by which apremilast exerts its therapeutic action is not well defined.

12.2 Pharmacodynamics

In clinical studies, apremilast decreased IL-17, IL-22 and TNF-alpha levels circulating in blood and reduced expression of these pro-inflammatory cytokine genes in skin. The clinical implications of these pharmacodynamic responses remain unclear.

12.3 Pharmacokinetics

Absorption

OTEZLA when taken orally is absorbed with an absolute bioavailability of ~73%, with peak plasma concentrations (Cmax) occurring at a median time (tmax) of ~2.5 hours. Co-administration with food does not alter the extent of absorption of OTEZLA.

OTEZLA XR when taken orally is absorbed with peak plasma concentrations (Cmax) occurring at a median time (tmax) of ~6 hours. OTEZLA XR 75 mg administered once daily demonstrates comparable PK exposure (steady-state AUC and Cmax) to OTEZLA 30 mg twice daily. When administered with a high-fat meal, OTEZLA XR tmax was delayed by 3 hours and Cmax and AUC were increased by ~28% compared to fasted conditions. Therefore, OTEZLA XR may be taken without regard to meals.

Distribution

Human plasma protein binding of apremilast is approximately 68%. Mean apparent volume of distribution (Vd) is 87 L.

Metabolism

Following oral administration in humans, apremilast is a major circulating component (45%) followed by inactive metabolite M12 (39%), a glucuronide conjugate of O-demethylated apremilast. It is extensively metabolized in humans with up to 23 metabolites identified in plasma, urine and feces. Apremilast is metabolized by both cytochrome (CYP) oxidative metabolism with subsequent glucuronidation and non-CYP mediated hydrolysis. In vitro, CYP metabolism of apremilast is primarily mediated by CYP3A4, with minor contributions from CYP1A2 and CYP2A6.

Elimination

The plasma clearance of apremilast is about 10 L/hr in healthy subjects, with a terminal elimination half-life of approximately 6-9 hours. Following oral administration of radiolabeled apremilast, about 58% and 39% of the radioactivity is recovered in urine and feces, respectively, with about 3% and 7% of the radioactive dose recovered as apremilast in urine and feces, respectively.

Specific Populations

Patients with Hepatic Impairment: The pharmacokinetics of apremilast is not affected by moderate or severe hepatic impairment.

Patients with Renal Impairment: The pharmacokinetics of apremilast is not affected by mild or moderate renal impairment. In 8 adult subjects with severe renal impairment administered a single dose of 30 mg OTEZLA, the AUC and Cmax of apremilast increased by approximately 88% and 42%, respectively [see Dosage and Administration (2.3) and Use in Specific Populations (8.6)].

The effects of renal impairment have not been studied for OTEZLA XR [see Dosage and Administration (2.3) and Use in Specific Populations (8.6)].

Geriatric Patients: A single oral dose of 30-mg apremilast was studied in young adults and elderly healthy subjects. The apremilast exposure in elderly subjects (65 to 85 years of age) was about 13% higher in AUC and about 6% higher in Cmax than in young subjects (18 to 55 years of age) [see Use in Specific Populations (8.5)].

Pediatric Patients: The pharmacokinetics of OTEZLA were evaluated in a clinical trial in pediatric subjects 6 to 17 years of age with moderate to severe plaque psoriasis at the recommended pediatric dosage regimen [see Dosage and Administration (2.1) and Clinical Studies (14.3)]. Population pharmacokinetic analysis indicated that steady-state exposure (AUC and Cmax) of OTEZLA in pediatric subjects receiving the pediatric maintenance dosage regimen (20 or 30 mg twice daily, based on body weight) was comparable to steady-state exposure in adult subjects at the 30 mg twice daily dosage.

Male and Female Patients: In pharmacokinetic trials in healthy volunteers, the extent of exposure in females was about 31% higher and Cmax was about 8% higher than that in male subjects.

Racial or Ethnic Groups: The pharmacokinetics of apremilast in Chinese and Japanese healthy male subjects is comparable to that in White healthy male subjects. In addition, apremilast exposure is similar among White subjects (including Hispanic or Latino and not Hispanic or Latino subjects) and Black or African American subjects.

Drug Interactions

In vitro data: Apremilast is not an inhibitor of CYP1A2, CYP2A6, CYP2B6, CYP2C8, CYP2C9, CYP2C19, CYP2D6, CYP2E1, or CYP3A4 and not an inducer of CYP1A2, CYP2B6, CYP2C9, CYP2C19, or CYP3A4. Apremilast is a substrate, but not an inhibitor of P-glycoprotein (P-gp) and is not a substrate or an inhibitor of organic anion transporter (OAT)1 and OAT3, organic cation transporter (OCT)2, organic anion transporting polypeptide (OATP)1B1 and OATP1B3, or breast cancer resistance protein (BCRP).

Drug interaction trials were performed with apremilast and CYP3A4 substrates (oral contraceptive containing ethinyl estradiol and norgestimate), CYP3A and P-gp inhibitor (ketoconazole), CYP450 inducer (rifampin) and frequently co-administered drug in this patient population (methotrexate).

No significant pharmacokinetic interactions were observed when 30-mg oral apremilast was administered with either oral contraceptive, ketoconazole, or methotrexate. Co-administration of the CYP450 inducer rifampin (600 mg once daily for 15 days) with a single oral dose of 30-mg apremilast resulted in reduction of apremilast AUC and Cmax by 72% and 43%, respectively [see Warnings and Precautions (5.5) and Drug Interactions (7.1)].

13 NONCLINICAL TOXICOLOGY

13.1 Carcinogenesis, Mutagenesis, Impairment of Fertility

Long-term studies were conducted in mice and rats with apremilast to evaluate its carcinogenic potential. No evidence of apremilast-induced tumors was observed in mice at oral doses up to approximately 9-times the MRHD on an AUC basis (1000 mg/kg/day) or in rats at oral doses up to approximately 0.08- and 1.1-times the MRHD, (20 mg/kg/day in males and 3 mg/kg/day in females, respectively).

Apremilast tested negative in the Ames assay, in vitro chromosome aberration assay of human peripheral blood lymphocytes, and the in vivo mouse micronucleus assay.

In a fertility study of male mice, apremilast at oral doses up to approximately 3-times the MRHD based on AUC (up to 50 mg/kg/day) produced no effects on male fertility. In a fertility study of female mice, apremilast was administered at oral doses of 10, 20, 40, or 80 mg/kg/day. At doses ≥ 1.8-times the MRHD (≥ 20 mg/kg/day), estrous cycles were prolonged, due to lengthening of diestrus which resulted in a longer interval until mating. Mice that became pregnant at doses of 20 mg/kg/day and greater also had increased incidences of early post-implantation losses. There was no effect of apremilast approximately 1.0-times the MRHD (10 mg/kg/day).

14 CLINICAL STUDIES

14.1 Adult Psoriatic Arthritis

The safety and efficacy of OTEZLA was evaluated in three multicenter, randomized, double-blind, placebo-controlled trials (PsA-1 [NCT01172938], PsA-2 [NCT01212757], and PsA-3 [NCT01212770]) of similar design. A total of 1493 adult subjects with active PsA (≥ 3 swollen joints and ≥ 3 tender joints) despite prior or current treatment with disease-modifying antirheumatic drug (DMARD) therapy were randomized. Subjects enrolled in these trials had a diagnosis of PsA for at least 6 months. One qualifying psoriatic skin lesion of at least 2 cm in diameter was required in Trial PsA-3. Previous treatment with a biologic, including TNF blockers was allowed (up to 10% could be TNF blocker therapeutic failures). Across the three trials, subjects were randomly assigned to placebo (n = 496), OTEZLA 20 mg (n = 500), or OTEZLA 30 mg (n = 497) given orally twice daily. Titration was used over the first 5 days [see Dosage and Administration (2.1)]. Subjects were allowed to receive stable doses of concomitant methotrexate [MTX (≤ 25 mg/week)], sulfasalazine [SSZ (≤ 2 g/day)], leflunomide [LEF (≤ 20 mg/day)], low dose oral corticosteroids (equivalent to ≤ 10 mg of prednisone a day), and/or nonsteroidal anti-inflammatory drugs (NSAIDs) during the trial. Treatment assignments were stratified based on small molecule DMARD use at baseline in Trials PsA-1, PsA-2 and PsA-3. There was an additional stratification of body surface area (BSA) > 3% with psoriasis in Trial PsA-3. The subjects who were therapeutic failures of > 3 agents for PsA (small molecules or biologics), or > 1 biologic TNF blocker were excluded.

The primary endpoint was the percentage of subjects achieving American College of Rheumatology (ACR) 20 response at Week 16. Placebo-controlled efficacy data were collected and analyzed through Week 24. Subjects whose tender and swollen joint counts had not improved by at least 20% were considered non-responders at Week 16. Placebo non-responders were re-randomized 1:1 in a blinded fashion to either OTEZLA 20 mg twice daily or 30 mg twice daily following the titration schema [see Dosage and Administration (2.1)]. OTEZLA subjects remained on their initial treatment. At Week 24, all remaining placebo subjects were re-randomized to either 20 mg twice daily or 30 mg twice daily.

Subjects with subtypes of PsA were enrolled across the three trials, including symmetric polyarthritis (62.0%), asymmetric oligoarthritis (27.0%), distal interphalangeal (DIP) joint arthritis (6.0%), arthritis mutilans (3.0%), and predominant spondylitis (2.1%). The median duration of PsA disease was 5 years. Subjects received concomitant therapy with at least one DMARD (65.0%), MTX (55.0%), SSZ (9.0%), LEF (7.0%), low dose oral corticosteroids (14.0%), and NSAIDs (71.0%). Prior treatment with small molecule DMARDs only was reported in 76.0% of subjects and prior treatment with biologic DMARDs was reported in 22.0% of subjects, which includes 9.0% who had failed prior biologic DMARD treatment.

Clinical Response in Subjects with Psoriatic Arthritis

The percent of subjects achieving ACR 20, 50 and 70 responses in Trials PsA-1, PsA-2, and PsA-3 are presented in Table 6 below. OTEZLA ± DMARDs, compared with Placebo ± DMARDs resulted in a greater improvement in signs and symptoms of psoriatic arthritis as demonstrated by the proportion of subjects with an ACR 20 response at Week 16.

Table 6. Proportion of Adult Subjects With Active Psoriatic Arthritis With ACR Responses in Trials PsA-1, PsA-2 and PsA-3
 | PsA-1 |  | PsA-2 |  | PsA-3
N [N is number of randomized and treated subjects.] | Placebo ± DMARDs N = 168 | OTEZLA 30 mg twice daily ± DMARDs N = 168 | Placebo ± DMARDs N = 159 | OTEZLA 30 mg twice daily ± DMARDs N = 162 | Placebo ± DMARDs N = 169 | OTEZLA 30 mg twice daily ± DMARDs N = 167
ACR 20 Week 16 | 19% | 38% [Statistically significantly different from placebo (p < 0.05).] | 19% | 32% | 18% | 41%
ACR 50 Week 16 | 6% | 16% | 5% | 11% | 8% | 15%
ACR 70 Week 16 | 1% | 4% | 1% | 1% | 2% | 4%

OTEZLA 30 mg twice daily resulted in improvement for each ACR component, compared to placebo at Week 16 in Trial PsA-1 (Table 7). Consistent results were observed in Trials PsA-2 and PsA-3.

Table 7. ACR Components Mean Change from Baseline at Week 16 in Trial PsA-1
 | Placebo (N [N reflects randomized subjects; actual number of subjects evaluable for each endpoint may vary by timepoint.] = 168) | OTEZLA 30 mg twice daily (N = 168)
Number of tender joints [Scale 0-78.]
Sample Size | 166 | 164
Baseline | 23 | 23
Mean Change at Week 16 | -2 | -7
Number of swollen joints [Scale 0-76.]
Sample Size | 166 | 164
Baseline | 13 | 13
Mean Change at Week 16 | -2 | -5
Patient's assessment of pain [VAS = Visual Analog Scale; 0 = best, 100 = worst.]
Sample Size | 165 | 159
Baseline | 61 | 58
Mean Change at Week 16 | -6 | -14
Patient's global assessment of disease activity
Sample Size | 165 | 159
Baseline | 59 | 56
Mean Change at Week 16 | -3 | -10
Physician's global assessment of disease activity
Sample Size | 158 | 159
Baseline | 55 | 56
Mean Change at Week 16 | -8 | -19
HAQ-DI [HAQ-DI = Health Assessment Questionnaire – Disability Index; 0 = best, 3 = worst; measures the subject's ability to perform the following: dress/groom, arise, eat, walk, reach, grip, maintain hygiene, and maintain daily activity.] score
Sample Size | 165 | 159
Baseline | 1.2 | 1.2
Mean Change at Week 16 | -0.09 | -0.2
CRP [CRP = C-reactive protein; Reference range 00.5 mg/dL.]
Sample Size | 166 | 167
Baseline | 1.1 | 0.8
Mean Change at Week 16 | 0.1 | -0.1
Mean changes from baseline are least square means from analyses of covariance.

Treatment with OTEZLA resulted in improvement in dactylitis and enthesitis in subjects with pre-existing dactylitis or enthesitis.

Physical Function Response

OTEZLA 30 mg twice daily demonstrated a greater improvement compared to placebo in mean change from baseline for the Health Assessment Questionnaire Disability Index (HAQDI) score at Week 16 [0.244 vs. 0.086, respectively; 95% CI for the difference was (0.26, 0.06)] in Trial PsA1. The proportions of HAQDI responders (≥ 0.3 improvement from baseline) at Week 16 for the OTEZLA 30 mg twice daily group were 38%, compared to 27%, for the placebo group in Trial PsA1. Consistent results were observed in Trials PsA2 and PsA3.

14.2 Adult Moderate to Severe Plaque Psoriasis

Two multicenter, randomized, double-blind, placebo-controlled trials (PSOR-1 [NCT01194219] and PSOR-2 [NCT01232283]) enrolled a total of 1257 subjects 18 years of age and older with moderate to severe plaque psoriasis [body surface area (BSA) involvement of ≥ 10%, static Physician Global Assessment (sPGA) of ≥ 3 (moderate or severe disease), Psoriasis Area and Severity Index (PASI) score ≥ 12, candidates for phototherapy or systemic therapy]. Subjects were allowed to use low potency topical corticosteroids on the face, axilla and groin. Subjects with plaque psoriasis of the scalp were allowed to use coal tar shampoo and/or salicylic acid scalp preparations on scalp lesions.

Trial PSOR-1 enrolled 844 subjects and Trial PSOR-2 enrolled 413 subjects. In both trials, subjects were randomized 2:1 to OTEZLA 30 mg twice daily (BID) or placebo for 16 weeks. Both trials assessed the proportion of subjects who achieved PASI-75 at Week 16 and the proportion of subjects who achieved an sPGA score of clear (0) or almost clear (1) at Week 16. Across both trials, subjects ranged in age from 18 to 83 years, with an overall median age of 46 years. The mean baseline BSA involvement was 25.2% (median 21.0%), the mean baseline PASI score was 19.1 (median 16.8), and the proportion of subjects with an sPGA score of 3 (moderate) and 4 (severe) at baseline were 70.0% and 29.8%, respectively. Approximately 30% of all subjects had received prior phototherapy and 54% had received prior conventional systemic and/or biologic therapy for the treatment of psoriasis with 37% receiving prior conventional systemic therapy and 30% receiving prior biologic therapy. Approximately one-third of subjects had not received prior phototherapy, conventional systemic nor biologic therapy. A total of 18% of subjects had a history of psoriatic arthritis.

Clinical Response in Adult Subjects with Moderate to Severe Plaque Psoriasis

The proportion of subjects who achieved PASI-75 responses, and an sPGA score of clear (0) or almost clear (1), are presented in Table 8.

Table 8. Clinical Response at Week 16 in Adults with Moderate to Severe Plaque Psoriasis in Trials PSOR-1 and PSOR-2
 | Trial PSOR-1 |  | Trial PSOR-2
 | Placebo | OTEZLA 30 mg BID | Placebo | OTEZLA 30 mg BID [BID = twice daily.]
N [N is number of randomized and treated subjects.] | N = 282 | N = 562 | N = 137 | N = 274
PASI [PASI = Psoriasis Area and Severity Index.] -75, n (%) | 15 (5.3) | 186 (33.1) | 8 (5.8) | 79 (28.8)
sPGA [sPGA = Static Physician Global Assessment.] of Clear or Almost Clear, n (%) | 11 (3.9) | 122 (21.7) | 6 (4.4) | 56 (20.4)

The median time to loss of PASI-75 response among the subjects re-randomized to placebo at Week 32 during the Randomized Treatment Withdrawal Phase was 5.1 weeks.

Plaque Psoriasis Involving the Scalp Area

A randomized, double-blind, placebo-controlled trial (PSOR-3 [NCT03123471]) was conducted in 303 adult subjects with moderate to severe plaque psoriasis of the scalp. Enrolled subjects had a Scalp Physician Global Assessment (ScPGA) score of ≥ 3, Scalp Surface Area (SSA) involvement of ≥ 20%, an inadequate response or intolerance to at least one topical therapy for plaque psoriasis of the scalp, and moderate to severe plaque psoriasis (BSA involvement of ≥ 10%, sPGA of ≥ 3 [moderate or severe disease], and PASI score ≥ 12).

Subjects were randomized 2:1 to receive either OTEZLA 30 mg twice daily (n = 201) or placebo twice daily (n = 102) for 16 weeks. The primary endpoint was the proportion of subjects who achieved an ScPGA response at Week 16 (defined as ScPGA score of clear [0] or almost clear [1] with at least a 2-point reduction from baseline at Week 16). Secondary endpoints included the proportion of subjects with Whole Body Itch Numeric Rating Scale (NRS) response (defined as ≥ 4-point reduction from baseline) and the proportion of subjects with a Scalp Itch NRS response (defined as ≥ 4-point reduction from baseline).

Subjects had a mean age of 46.9 years, 61.7% were men and 75.6% were white. At baseline, 76.9% of subjects had moderate plaque psoriasis of the scalp (ScPGA of 3), 23.1% had severe plaque psoriasis of the scalp (ScPGA of 4), 71.6% of subjects were biologic-naïve, and 58.8% had failed 1 or 2 topical treatments. At baseline, the mean Whole Body Itch NRS score was 7.2 and the mean Scalp Itch NRS score was 6.7 with the scales ranging from 0 to 10. The mean baseline SSA involvement was 60.6% and the mean baseline BSA involvement was 19.8%.

The proportion of subjects who achieved an ScPGA response, Whole Body Itch NRS response, and Scalp Itch NRS response at Week 16 are presented in Table 9.

Figure 1 displays the proportion of subjects achieving Whole Body Itch NRS response at each visit, while Figure 2 displays the proportion of subjects achieving Scalp Itch NRS response at each visit.

Table 9. Efficacy Results at Week 16 in Adults with Plaque Psoriasis of the Scalp in Trial PSOR-3
 | Trial PSOR-3
 | Placebo | OTEZLA 30 mg twice daily | Treatment Difference [OTEZLA – Placebo.] , [Adjusted difference in proportions is the weighted average of the treatment differences across baseline ScPGA scores with the Cochran-Mantel-Haenszel weights.] (95% CI [CI = confidence interval.])
Number of subjects randomized | N = 102 | N = 201
ScPGA response [ScPGA score of clear [0] or almost clear [1] with at least a 2-point reduction from baseline.] | 13.7% | 43.3% | 29.6% (19.5%, 39.7%)
Number of subjects with baseline Whole Body Itch NRS Score ≥ 4 | N = 94 | N = 185
Whole Body Itch NRS response | 22.5% | 45.5% | 23.0% (11.5%, 34.6%)
Number of subjects with baseline Scalp Itch NRS Score ≥ 4 | N = 90 | N = 175
Scalp Itch NRS response | 21.1% | 47.1% | 26.2% (13.9%, 38.5%)

Figure 1. Proportion (± SE) of Subjects Achieving Whole Body Itch NRS Response through Week 16

NRS = Numeric Rating Scale; SE = standard error

Figure 2. Proportion (± SE) of Subjects Achieving Scalp Itch NRS Response through Week 16

NRS = Numeric Rating Scale; SE = standard error

Plaque Psoriasis Involving the Genital Area

A randomized, double-blind, placebo-controlled trial (PSOR-5 [NCT03777436]) was conducted in 289 adult subjects with moderate to severe plaque psoriasis of the genital area. Subjects had a modified static Physician Global Assessment of Genitalia (sPGA-G) score of ≥ 3 (moderate or severe), sPGA score of ≥ 3 (moderate or severe), and had an inadequate response or were intolerant to topical therapy for the treatment of plaque psoriasis of the genital area.

Subjects were randomized 1:1 to receive either apremilast 30 mg twice daily (n = 143) or placebo twice daily (n = 146) for 16 weeks. At Week 16, the placebo group was switched to receive OTEZLA and the OTEZLA group remained on drug through Week 32. The primary endpoint was the proportion of subjects who achieved a modified sPGA-G response (defined as a score of clear [0] or almost clear [1] with at least a 2-point reduction from baseline) at Week 16. Secondary endpoints included the proportion of subjects who achieved an sPGA response (defined as a score of clear [0] or almost clear [1] with at least a 2-point reduction from baseline) at Week 16 and the proportion of subjects who achieved at least a 4-point improvement in the 11-point Genital Psoriasis Itch Numeric Rating Scale (GPI-NRS) item score within the Genital Psoriasis Symptoms Scale (GPSS) at Week 16, among subjects with a baseline GPI-NRS score of ≥ 4.

Subjects ranged in age from 18-81 years, with a median age of 44 years. The proportions of subjects with a modified sPGA-G score of 3 (moderate) and 4 (severe) at baseline were 86.9% and 13.1%, respectively. The proportions of subjects with a sPGA score of 3 (moderate) and 4 (severe) at baseline were 88.6% and 11.1%, respectively. Baseline BSA involvement was < 10% for 57.4% of the subjects and ≥ 10% for 42.6% of the subjects. The mean baseline GPI-NRS score was 6.5. Of the enrolled subjects, 78.9% did not receive prior conventional systemic therapy and 84.4% were biologic-naïve.

The proportions of subjects who achieved a modified sPGA-G response, sPGA response, and GPI-NRS response are presented in Table 10.

Table 10. Efficacy Results at Week 16 in Adults with Plaque Psoriasis of the Genital Area in Trial PSOR-5
 | Trial PSOR-5
 | Placebo | OTEZLA 30 mg twice daily | Treatment Difference [OTEZLA – Placebo.] , [Adjusted difference in proportions is the weighted average of the treatment differences across the baseline BSA strata (BSA < 10% or ≥ 10%) with the Cochran-Mantel-Haenszel weights.] (95% CI) [CI = confidence interval.]
Number of Subjects Randomized | N = 146 | N = 143
Modified sPGA-G Response [Modified sPGA-G score of clear [0] or almost clear [1] with at least a 2-point reduction from baseline. The sPGA-G scale was modified from a 6-point to a 5-point scale, ranging from 0 (clear) to 4 (severe), to assess the severity of the 3 primary signs of genital psoriasis: erythema, scaling, and plaque elevation.] | 19.5% | 39.6% | 20.1% (9.2%, 30.9%)
sPGA Response [sPGA score of clear [0] or almost clear [1] with at least a 2-point reduction from baseline.] | 6.9% | 22.2% | 15.2% (6.9%, 23.6%)
Number of Subjects with Baseline GPI-NRS Score ≥ 4 | N = 121 | N = 122
GPI-NRS Response [GPI-NRS score reduction of ≥ 4-points from baseline.] | 19.6% | 47.3% | 27.4% (15.4%, 39.3%)

14.3 Pediatric Moderate to Severe Plaque Psoriasis

A multicenter, randomized, double-blind, placebo-controlled trial (PSOR-6 [NCT03701763]) was conducted in 245 pediatric subjects 6 to 17 years of age (inclusive) with moderate to severe plaque psoriasis who were candidates for phototherapy or systemic therapy. Subjects had an sPGA score of ≥ 3 (moderate or severe disease), BSA involvement of ≥ 10%, and PASI score of ≥ 12, with psoriasis that was inadequately controlled by or inappropriate for topical therapy. Subjects were allowed to use low potency or weak topical corticosteroids on the face, axilla, and groin and unmedicated skin moisturizers for body lesions only.

Subjects were randomized 2:1 to receive either OTEZLA (n = 163) or placebo (n = 82) for 16 weeks. Subjects with a baseline weight of 20 kg to < 50 kg received OTEZLA 20 mg twice daily or placebo twice daily, and subjects with a baseline weight ≥ 50 kg received OTEZLA 30 mg twice daily or placebo twice daily. At Week 16, the placebo group was switched to receive OTEZLA (with dosage based on baseline weight) and the OTEZLA group remained on drug (according to their original dosing assignment) through Week 52. The primary endpoint was the proportion of subjects who achieved an sPGA response (defined as a score of clear [0] or almost clear [1] with at least a 2-point reduction from baseline) at Week 16. The key secondary endpoint was the proportion of subjects who achieved a PASI-75 response (at least a 75% reduction in PASI score from baseline) at Week 16.

Enrolled subjects ranged in age from 6 to 17 years, with a median age of 13 years; 41.2% of subjects were 6 to 11 years of age and 58.8% of subjects were 12 to 17 years of age. Of the enrolled subjects, 52.2% were female. For race, 86.9% were White, 3.7% were Asian, 3.3% were Black or African American, 0.8% were American Indian or Alaskan Native, and 5.3% were not reported or unknown. For ethnicity, 81.6% of subjects identified as not Hispanic or Latino, 13.1% identified as Hispanic or Latino, and 5.3% were not reported or unknown. The mean baseline BSA involvement was 31.5% (median 26.0%), the mean baseline PASI score was 19.8 (median 17.2), and the proportions of subjects with an sPGA score of 3 (moderate) and 4 (severe) at baseline were 75.5% and 24.5%, respectively. Of the enrolled subjects, 82.9% did not receive prior conventional systemic therapy and 94.3% were biologic-naïve.

Clinical Response in Pediatric Subjects 6 to 17 Years of Age and Weighing at Least 20 kg with Moderate to Severe Plaque Psoriasis

The proportions of subjects who achieved sPGA response and PASI-75 response at Week 16 are presented in Table 11.

Table 11. Efficacy Results at Week 16 in Pediatric Subjects 6 to 17 Years of Age and Weighing at Least 20 kg with Moderate to Severe Plaque Psoriasis in Trial PSOR-6
 | Trial PSOR-6
 | Placebo | OTEZLA [Subjects weighing ≥ 50 kg received OTEZLA 30 mg twice daily and subjects weighing 20 kg to < 50 kg received OTEZLA 20 mg twice daily.] | Treatment Difference [OTEZLA – Placebo.] , [Adjusted difference in proportions is the weighted average of the treatment differences across the baseline age strata (6 to 11 years of age or 12 to 17 years of age) with the Cochran-Mantel-Haenszel weights.] (95% CI) [CI = confidence interval.]
Number of Subjects Randomized | N = 82 | N = 163
sPGA Response [sPGA score of clear [0] or almost clear [1] with at least a 2-point reduction from baseline.] | 10.8% | 33.1% | 22.3% (12.2%, 32.4%)
PASI-75 Response [At least a 75% reduction in PASI score from baseline.] | 16.0% | 45.7% | 29.7% (17.9%, 41.6%)

14.4 Adult Mild to Moderate Plaque Psoriasis

A multicenter, randomized, double-blind, placebo-controlled trial (PSOR-4 [NCT03721172]) was conducted in 595 adult subjects with mild to moderate plaque psoriasis (BSA involvement of 2-15%, sPGA score of 2-3 [mild or moderate disease], and PASI score of 2-15). Enrolled subjects had an inadequate response or were intolerant to at least one topical therapy and had not received prior biologic therapy. Subjects were allowed to use unmedicated emollients for lesions on non-scalp areas of the body and non-medicated shampoos for lesions on the scalp.

Subjects were randomized 1:1 to receive either OTEZLA 30 mg twice daily (n = 297) or placebo twice daily (n = 298) for 16 weeks. At Week 16, the placebo group was switched to receive OTEZLA and the OTEZLA group remained on drug through Week 32. The primary endpoint was the proportion of subjects who achieved an sPGA response (defined as an sPGA score of clear [0] or almost clear [1] with at least a 2-point reduction from baseline) at Week 16. Subjects with mild disease (sPGA = 2 at baseline) were required to be clear (sPGA = 0) to achieve an sPGA response. Other evaluated endpoints include the proportion of subjects with a Whole Body Itch NRS response (defined as a ≥ 4-point reduction from baseline) at Week 16 among subjects with a baseline Whole Body Itch NRS ≥ 4 and the proportion of subjects with an ScPGA response (defined as an ScPGA score of clear [0] or almost clear [1] with at least a 2-point reduction from baseline) at Week 16 among subjects with a baseline ScPGA score ≥ 2.

Subjects ranged in age from 18 to 85 years, with an overall median age of 50 years. The mean baseline BSA involvement was 6.4%, the mean baseline PASI score was 6.5, and the proportions of subjects with an sPGA score of 2 (mild) and 3 (moderate) at baseline were 30.6% and 69.4%, respectively.

Clinical Response in Subjects with Mild to Moderate Plaque Psoriasis

The proportions of subjects who achieved an sPGA response, Whole Body Itch NRS response, and an ScPGA response at Week 16 are presented in Table 12.

Table 12. Efficacy Results at Week 16 in Adults with Mild to Moderate Plaque Psoriasis in Trial PSOR-4
 | Trial PSOR-4
 | Placebo | OTEZLA 30 mg twice daily | Treatment Difference [OTEZLA – Placebo.] , [Adjusted difference in proportions is the weighted average of the treatment differences across baseline sPGA scores with the Cochran-Mantel-Haenszel weights.] (95% CI [CI = confidence interval.])
Number of Subjects Randomized | N = 298 | N = 297
sPGA Response [sPGA score of clear [0] or almost clear [1] with at least a 2-point reduction from baseline.] | 4.1% | 21.6% | 17.5% (12.2%, 22.8%)
Number of Subjects with Baseline Whole Body Itch NRS Score ≥ 4 | N = 249 | N = 253
Whole Body Itch NRS Response [Whole Body Itch NRS score reduction of ≥ 4-points from baseline.] | 18.6% | 43.2% | 24.7% (16.5%, 32.8%)
Number of Subjects with Baseline ScPGA Score ≥ 2 | N = 199 | N = 212
ScPGA Response [ScPGA score of clear [0] or almost clear [1] with at least a 2-point reduction from baseline.] | 16.6% | 44.0% | 27.4% (18.6%, 36.3%)

14.5 Adult Oral Ulcers Associated with Behçet's Disease

A multicenter, randomized, placebo-controlled trial (BCT-002 [NCT02307513]) enrolled a total of 207 adult subjects with BD with active oral ulcers. Subjects were previously treated with at least one nonbiologic BD medication and were candidates for systemic therapy. Subjects met the International Study Group (ISG) Criteria for BD. Subjects had at least 2 oral ulcers at screening and at least 2 oral ulcers at randomization and without currently active major organ involvement. Concomitant treatment for BD was not allowed.

Subjects were randomized 1:1 to receive either OTEZLA 30 mg twice daily (n = 104) or placebo (n = 103) for 12 weeks. After Week 12, all subjects received OTEZLA 30 mg twice daily.

Efficacy was assessed based on the number and pain of oral ulcers.

Subjects ranged in age from 19 to 72 years, with a mean age of 40 years. The mean duration of BD was 6.84 years. All subjects had a history of recurrent oral ulcers that were currently active. Subjects had a history of skin lesions (98.6%), genital ulcers (90.3%), musculoskeletal manifestations (72.5%), ocular manifestations (17.4%), central nervous system (9.7%), gastrointestinal (GI) manifestations (9.2%) and vascular involvement (1.4%). The mean baseline oral ulcer counts were 4.2 and 3.9 in the OTEZLA and placebo groups, respectively.

Measures of Oral Ulcers

Improvements in measures of oral ulcers at Week 12 are presented in Table 13.

Table 13. Clinical Response of Oral Ulcers at Week 12 in Adult Subjects with BD in the BCT-002 Trial (ITT [ITT = intent to treat.] Population)
Endpoint | Placebo N = 103 | OTEZLA 30 mg twice daily N = 104 | Treatment Difference [OTEZLA – Placebo.] (95% CI [CI = confidence interval.])
Change [Mean changes from baseline are least square means from mixed effects-model for repeated measures, adjusting for sex, region, and baseline pain of oral ulcers as measured by the visual analog scale.] from baseline in the pain of oral ulcers as measured by VAS [VAS = visual analog scale; 0 = no pain, 100 = worst possible pain.] at Week 12 | −18.7 | −42.7 | −24.1 (−32.4, −15.7)
Proportion [Subjects for whom data are not available to determine response status are considered non-responders.] of subjects achieving oral ulcer complete response (oral ulcer-free) at Week 12 | 22.3% | 52.9% | 30.6% [Adjusted difference in proportions is the weighted average of the treatment differences across the 4 strata of combined sex and region factors with the Cochran-Mantel-Haenszel weights.] (18.1%, 43.1%)
Proportion of subjects achieving oral ulcer complete response (oral ulcer-free) by Week 6, and who remained oral ulcer-free for at least 6 additional weeks during the 12-week Placebo-controlled Treatment Phase | 4.9% | 29.8% | 25.1% (15.5%, 34.6%)
Daily average [Mean daily averages are least squares means from analysis of covariance, after adjusting for sex, region, and baseline number of oral ulcers.] , [Based on oral ulcer counts measured at baseline and at Weeks 1, 2, 4, 6, 8, 10, and 12.] number of oral ulcers during the 12-week Placebo-controlled Treatment Phase | 2.6 | 1.5 | −1.1 (−1.6, −0.7)

Figure 3 displays the mean number of oral ulcers for each treatment group at each visit, while Figure 4 displays the mean oral ulcer pain on a visual analog scale for each treatment group at each visit.

Figure 3. Mean (± SE) Number of Oral Ulcers by Time Point Through Week 12 (ITT Population)

Weeks | 0 | 1 | 2 | 4 | 6 | 8 | 10 | 12
Placebo, n | 103 | 98 | 97 | 93 | 91 | 86 | 83 | 82
OTEZLA 30 mg twice daily, n | 104 | 101 | 101 | 101 | 98 | 94 | 94 | 97
ITT = intent-to-treat; SE = standard error

Figure 4. Mean (± SE) Oral Ulcer Pain on a Visual Analog Scale by Time Point Through Week 12 (ITT Population)

Weeks | 0 | 1 | 2 | 4 | 6 | 8 | 10 | 12
Placebo, n | 101 | 95 | 96 | 91 | 90 | 85 | 82 | 81
OTEZLA 30 mg twice daily, n | 102 | 95 | 97 | 99 | 97 | 92 | 93 | 95
ITT = intent to treat; SE = standard error.
Oral ulcer pain was assessed on a 100-mm Visual Analog Scale with 0 = no pain and 100 = worst possible pain. Mean baseline Visual Analog Scale pain scores were 61.2 and 60.8 in the OTEZLA 30 mg twice daily treatment group and placebo treatment group, respectively.

16 HOW SUPPLIED/STORAGE AND HANDLING

OTEZLA is available as diamond-shaped, film-coated tablets in the following dosage strengths: 10 mg pink tablet engraved with "APR" on one side and "10" on the other side; 20 mg brown tablet engraved with "APR" on one side and "20" on the other side; 30 mg beige tablet engraved with "APR" on one side and "30" on the other side.

Tablets are supplied in the strengths and package configurations listed in Table 14.

Table 14. OTEZLA Package Configurations
Package configuration | Tablet strength | NDC number
Configurations for 30 mg BID Dosage
28-day treatment initiation pack | 55-tablet blister pack including tablets for titration and maintenance dosage: 4 tablets (10 mg each), 4 tablets (20 mg each), and 47 tablets (30 mg each) | 55513-369-55
60-count bottle | 30 mg | 55513-137-60
Configurations for 20 mg BID Dosage
28-day treatment initiation pack | 55-tablet blister pack including tablets for titration and maintenance dosage: 4 tablets (10 mg each) and 51 tablets (20 mg each) | 55513-508-55
60-count bottle | 20 mg | 55513-497-60

OTEZLA XR is available as 75 mg round, biconvex, pink, film-coated extended-release tablets with "APR 75" printed in black on one side and a hole or indentation on either side of the tablet, which may or may not be visible.

Tablets are supplied in the strengths and package configurations listed in Table 15.

Table 15. OTEZLA XR Package Configurations
Package configuration | Tablet strength | NDC number
28-day treatment initiation pack | 41-tablet blister titration pack including tablets for titration and maintenance dosage: OTEZLA: 4 tablets (10 mg each), 4 tablets (20 mg each), and 19 tablets (30 mg each) and OTEZLA XR: 14 tablets (75 mg each) | 55513-516-41
Bottles of 30 | OTEZLA XR: 30 tablets (75 mg each) | 55513-519-30

Storage and Handling

Store OTEZLA tablets below 30°C (86°F).

Store OTEZLA XR tablets between 20°C and 25°C (68°F and 77°F); excursions permitted between 15°C and 30°C (59°F and 86°F) [see USP Controlled Room Temperature].

17 PATIENT COUNSELING INFORMATION

- Administration Instructions
  Instruct patients to take OTEZLA/OTEZLA XR only as prescribed [see Dosage and Administration (2.1 and 2.3)]. Advise patients to take OTEZLA/OTEZLA XR with or without food. Instruct patients to swallow tablets whole and not to crush, split, or chew prior to swallowing [see Dosage and Administration (2.4)].
- Hypersensitivity
  Inform patients that hypersensitivity reactions can occur following administration of OTEZLA/OTEZLA XR. Instruct patients to contact their healthcare provider if they experience symptoms of an allergic reaction [see Warnings and Precautions (5.1)].
- Diarrhea, Nausea, and Vomiting
  Advise patients of the potential complications of severe diarrhea, nausea, or vomiting and instruct them to contact their healthcare provider if they experience these adverse reactions, especially if the patient is 65 years of age or older [see Warnings and Precautions (5.2)].
- Depression
  Inform patients that treatment with OTEZLA/OTEZLA XR is associated with an increased incidence of depression. Advise patients, their caregivers, and families of the need to be alert for the emergence or worsening of depression, suicidal thoughts or other mood changes, and if such changes occur to contact their healthcare provider [see Warnings and Precautions (5.3)].
- Weight Decrease
  Inform patients that treatment with OTEZLA/OTEZLA XR is associated with potential weight loss. Instruct patients or caregivers to have their or their child's weight monitored regularly and, if unexplained or clinically significant weight loss occurs, to contact their healthcare provider for evaluation of the weight loss [see Warnings and Precautions (5.4)].
- Pregnancy
  Advise pregnant patients and patients of reproductive potential of the potential risk to a fetus. Advise patients to inform their prescriber of a known or suspected pregnancy [see Use in Specific Populations (8.1)].
- Residual Tablet Shell
  Patients receiving OTEZLA XR may notice an inert tablet shell passing in the stool or via colostomy. Patients should be informed that the active medication has already been absorbed by the time the patient sees the inert tablet shell.

OTEZLA® (apremilast) tablets
OTEZLA XR™ (apremilast) extended-release tablets
Manufactured for:
Amgen Inc.
Thousand Oaks, CA 91320-1799 U.S.A

OTEZLA® and OTEZLA XR™ are trademarks of Amgen Inc.

https://pat.amgen.com/otezla

© 2014-2021, 2023-2025 Amgen Inc. All Rights Reserved.

<part number> v10

PRINCIPAL DISPLAY PANEL - 60 Tablet Bottle Label

NDC 55513-137-60

Otezla®
(apremilast) tablets

30 mg

Rx Only
60 Tablets

PRINCIPAL DISPLAY PANEL - 28 Day Treatment Initiation Pack

NDC 55513-369-55

Otezla®
(apremilast) tablets
10 mg, 20 mg, 30 mg

28 Day
Treatment
Initiation Pack

This pack contains the following
for titration over 5 days up to the
prescribed dose of 30 mg:

Four - 10 mg tablets
Four - 20 mg tablets
Forty-seven - 30 mg tablets

55 TABLETS

Rx Only

AMGEN®

PRINCIPAL DISPLAY PANEL - 14 Day Treatment Initiation Pack - 55513-485-95

NDC 55513-485-95

Otezla®
(apremilast) tablets
10 mg, 20 mg, 30 mg

14 Day
Treatment
Initiation Pack

SAMPLE - NOT FOR SALE

This pack contains the following
for titration over 5 days up to the
prescribed dose of 30 mg:

Four - 10 mg tablets
Four - 20 mg tablets
Nineteen - 30 mg tablets

27 TABLETS

Rx Only

AMGEN®

PRINCIPAL DISPLAY PANEL - 14 Day Treatment Initiation Pack - 55513-485-96

NDC 55513-485-96

14 Day Treatment
Initiation Pack

SAMPLE - NOT FOR SALE

Each pack contains the following for titration
over 5 days up to the prescribed dose of 30 mg:
Four - 10 mg tablets
Four - 20 mg tablets
Nineteen - 30 mg tablets
Five starter packs each containing 27 TABLETS

Rx Only

AMGEN®

Otezla®
(apremilast) tablets

PRINCIPAL DISPLAY PANEL - 60 Tablet Bottle Label

NDC 55513-497-60

Otezla®
(apremilast) tablets

20 mg

Rx Only

60 Tablets

PRINCIPAL DISPLAY PANEL - 28 Day Treatment Initiation Pack - 55513-508-55

NDC 55513-508-55

Otezla®
(apremilast) tablets
10 mg, 20 mg

28 Day
Treatment
Initiation Pack

This pack contains the following
for titration over 3 days up to the
prescribed dose of 20 mg:

Four - 10 mg tablets
Fifty-one - 20 mg tablets

55 TABLETS

Rx Only

AMGEN®

PRINCIPAL DISPLAY PANEL - 14 Day Treatment Initiation Pack - 55513-996-95

NDC 55513-996-95

14 Day Treatment
Initiation Pack

SAMPLE - NOT FOR SALE

Each pack contains the following for titration over
3 days up to the prescribed dose of 20 mg:
Four - 10 mg tablets
Twenty-three - 20 mg tablets
Three starter packs each containing 27 TABLETS

Rx Only

AMGEN®

Otezla®
(apremilast) tablets

PRINCIPAL DISPLAY PANEL - 14 Day Treatment Initiation Pack - 55513-996-96

NDC 55513-996-96

Otezla®
(apremilast) tablets
10 mg, 20 mg

14 Day
Treatment
Initiation Pack

SAMPLE - NOT FOR SALE

This pack contains the following
for titration over 3 days up to the
prescribed dose of 20 mg:

Four - 10 mg tablets
Twenty-three - 20 mg tablets

27 TABLETS

Rx Only

AMGEN®

PRINCIPAL DISPLAY PANEL - 75 mg Tablet Bottle Label

Once-daily
NDC 55513-519-30

Otezla XR™
(apremilast)
extended-release tablets

75 mg

Rx Only
30 Tablets

PRINCIPAL DISPLAY PANEL - 28 Day Treatment Initiation Pack - 55513-516-41

NDC 55513-516-41

Otezla®
(apremilast) tablets

10 mg, 20 mg, 30 mg

Otezla XR™
(apremilast)
extended-release tablets

75 mg

28 Day
Treatment
Initiation Pack

This pack contains the following for titration
up to 30 mg twice daily and transition to the
prescribed dose of 75 mg once daily.

Four - 10 mg tablets
Four - 20 mg tablets
Nineteen - 30 mg tablets
Fourteen - 75 mg extended-release tablets

Contains a total of 41 tablets.

Rx Only
AMGEN